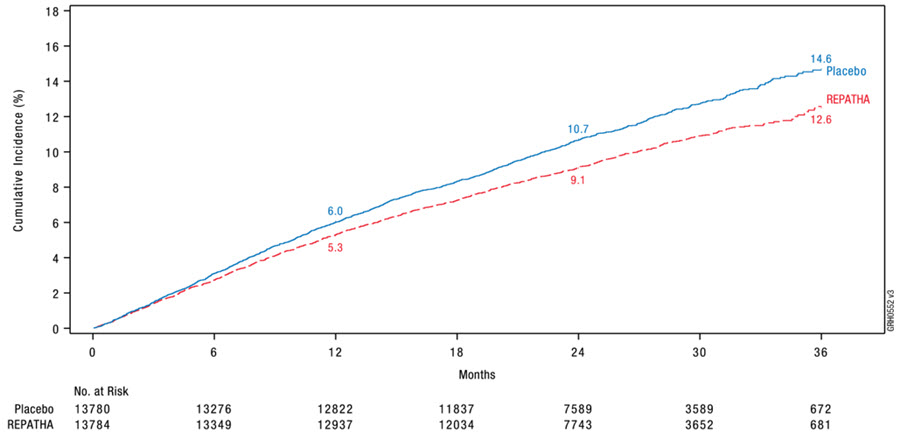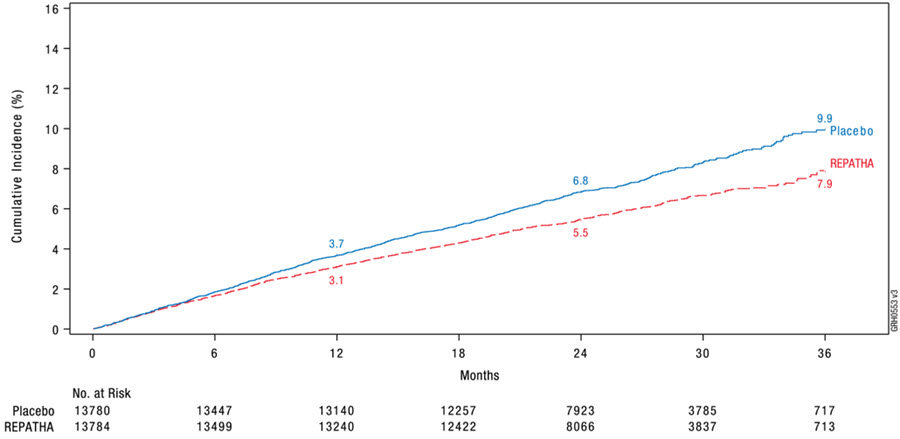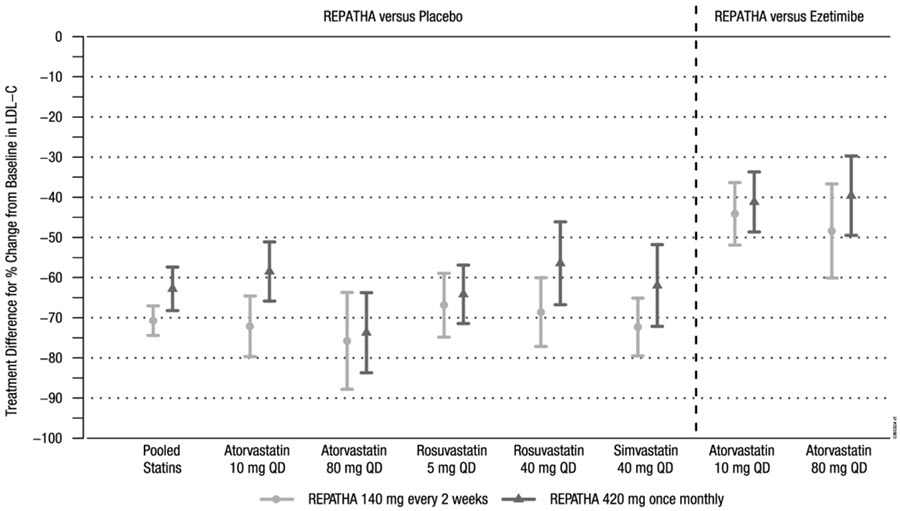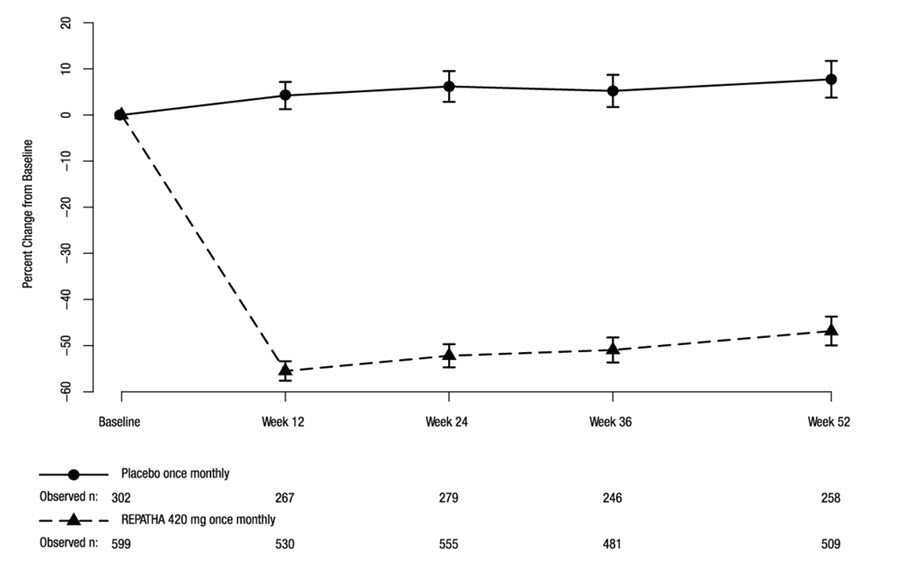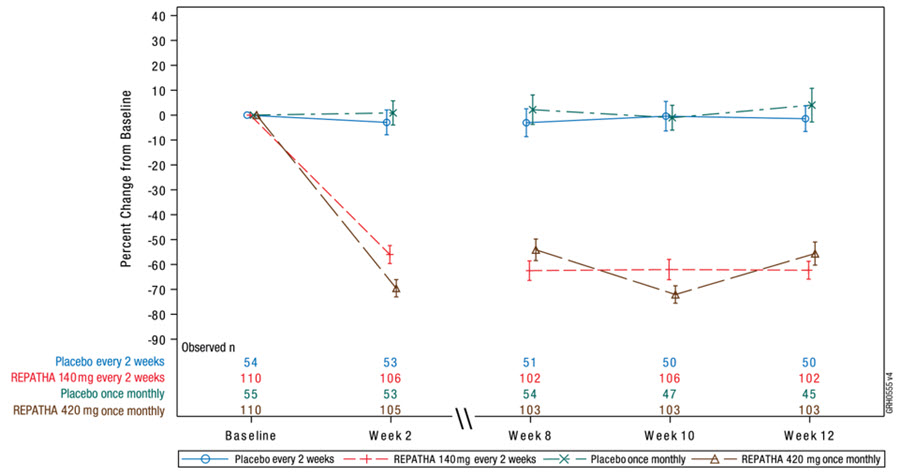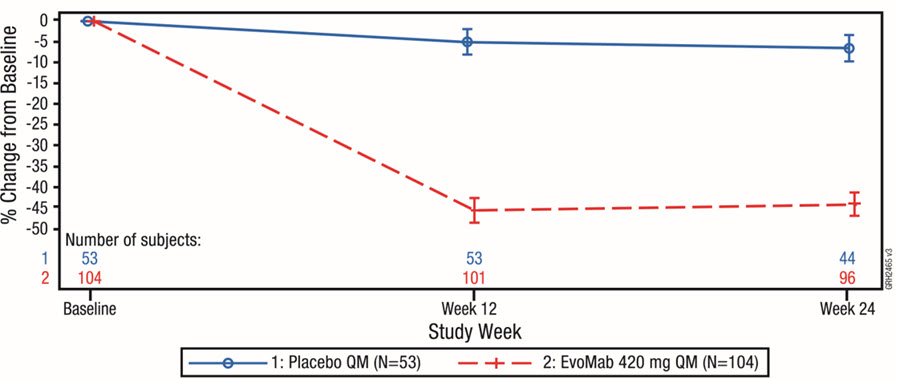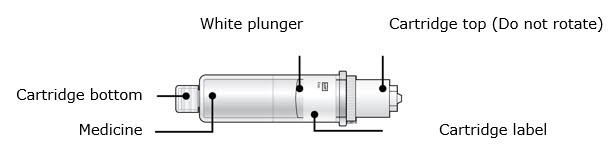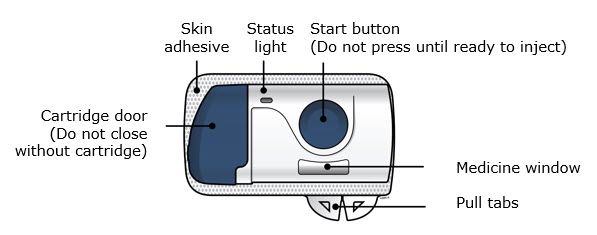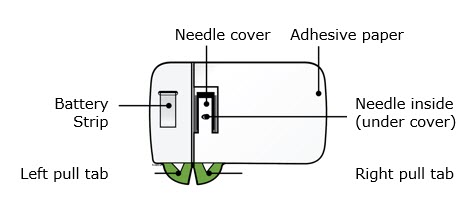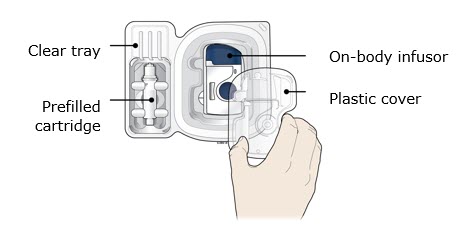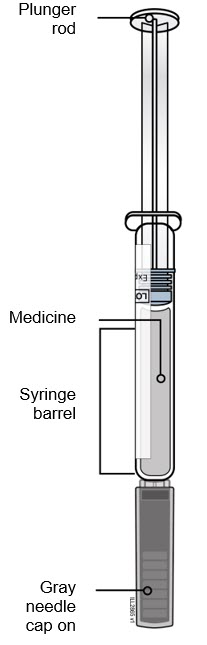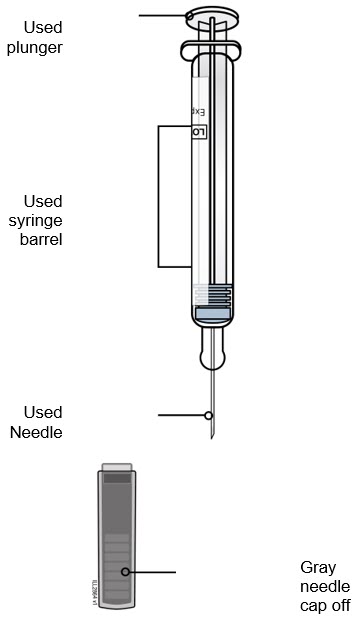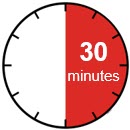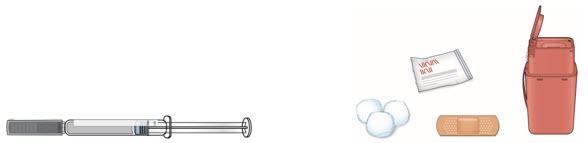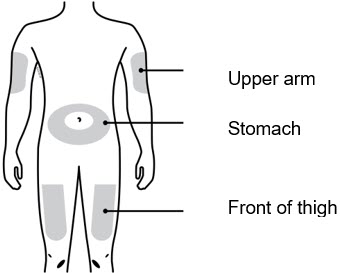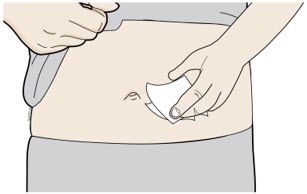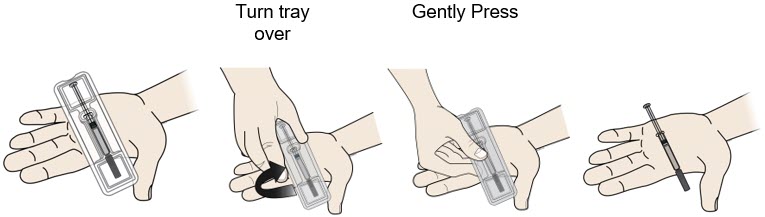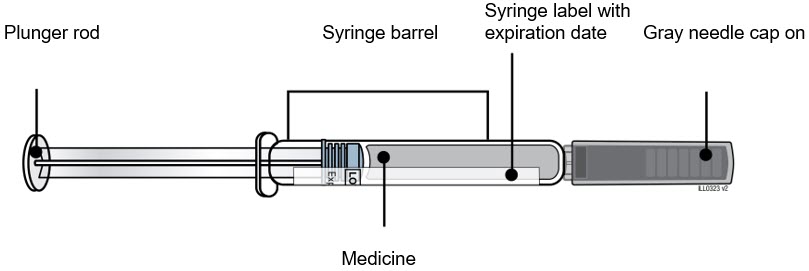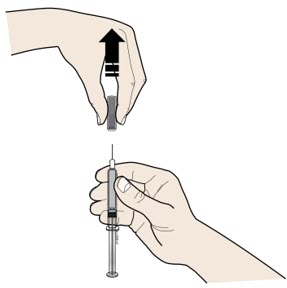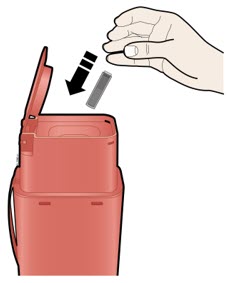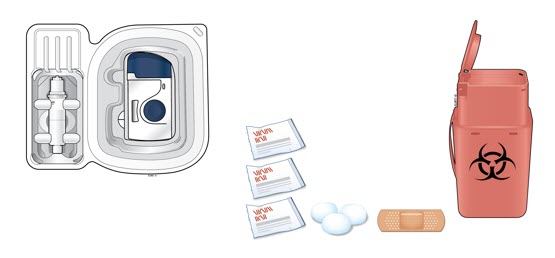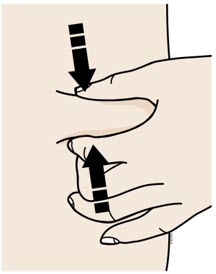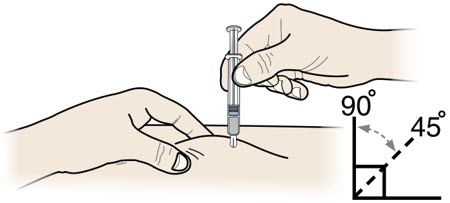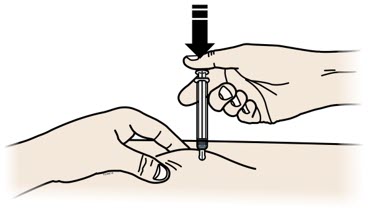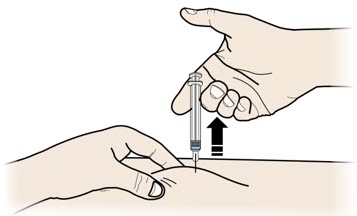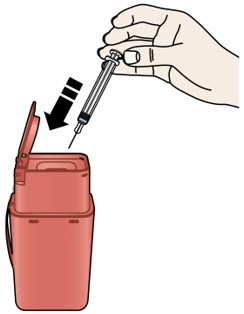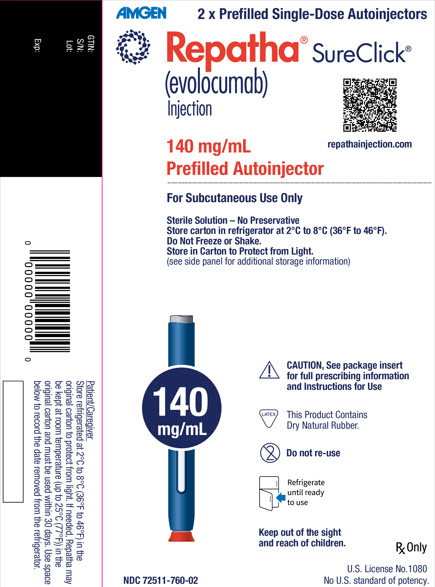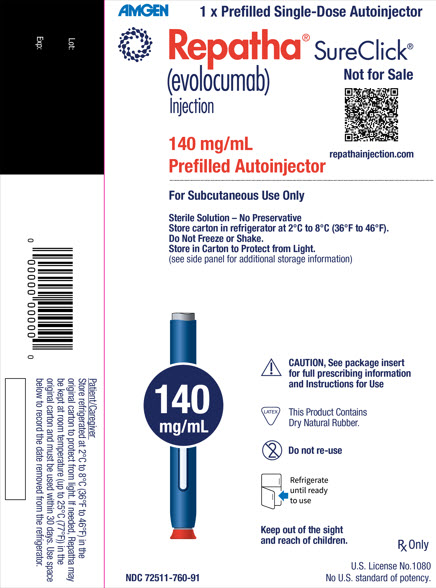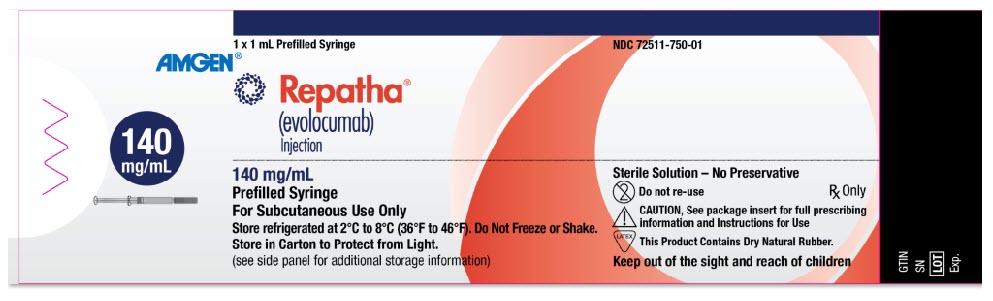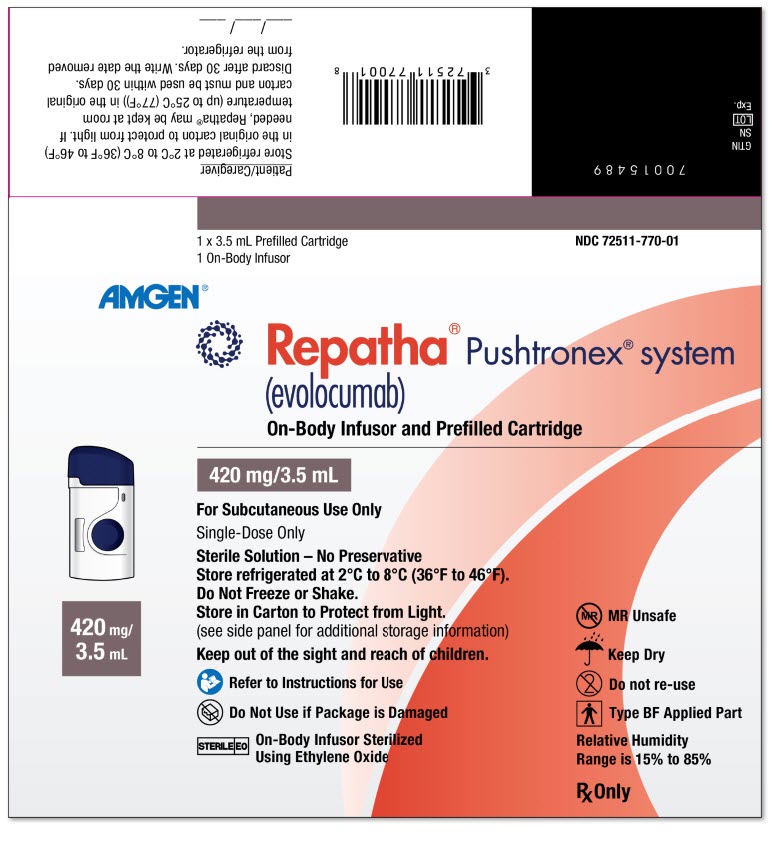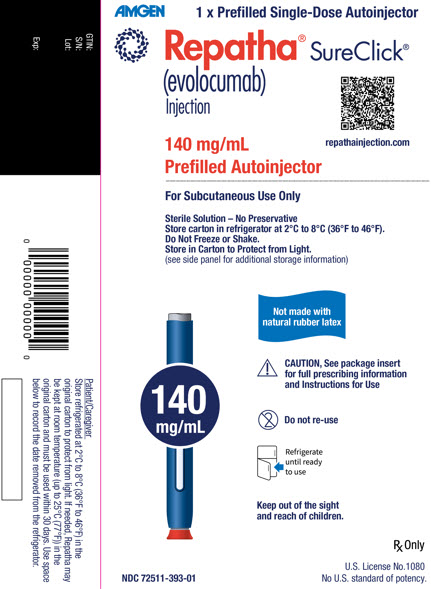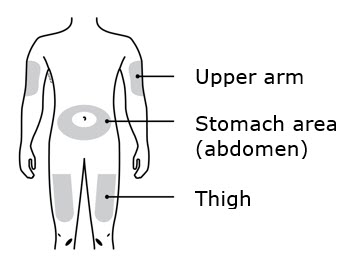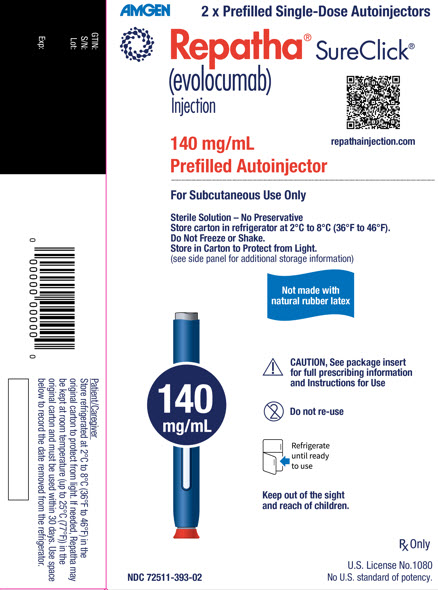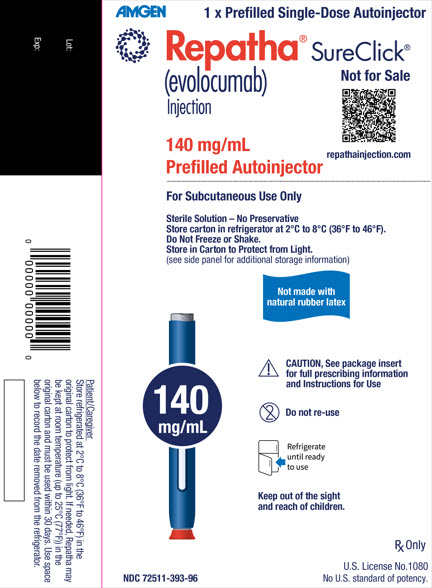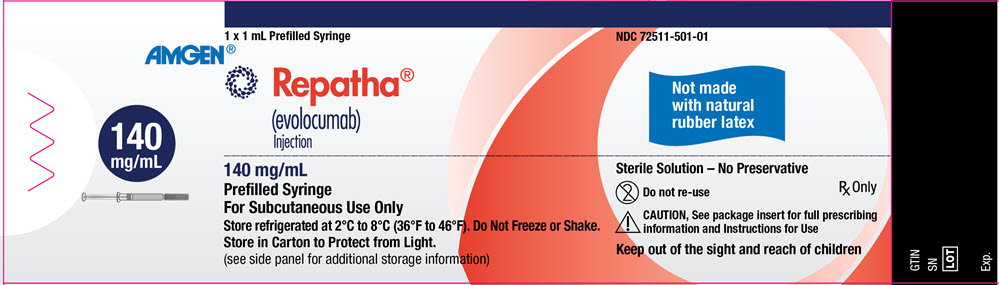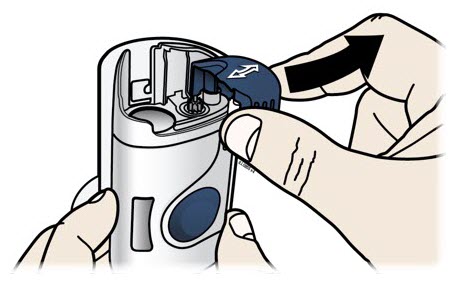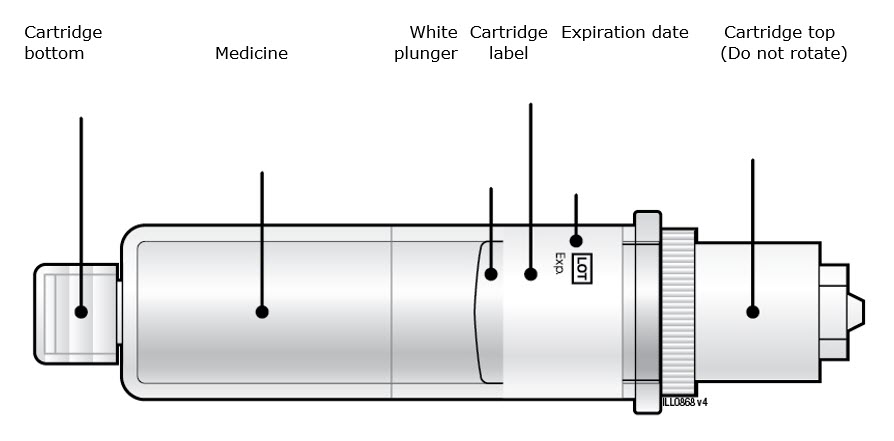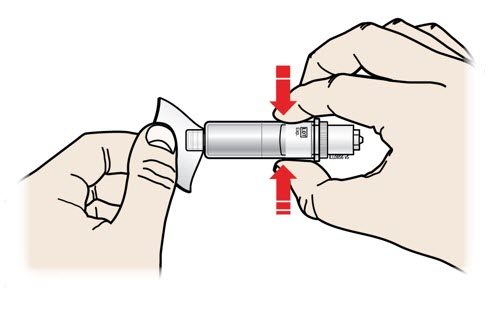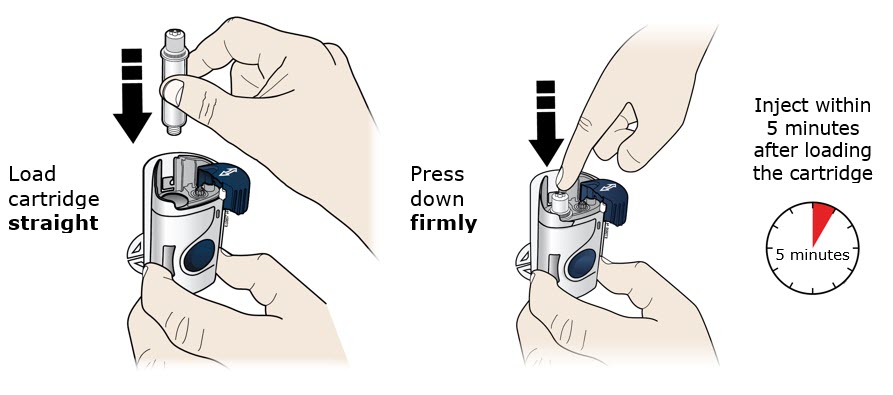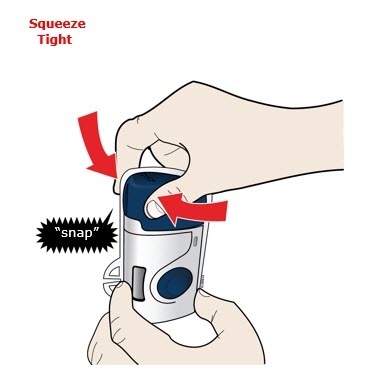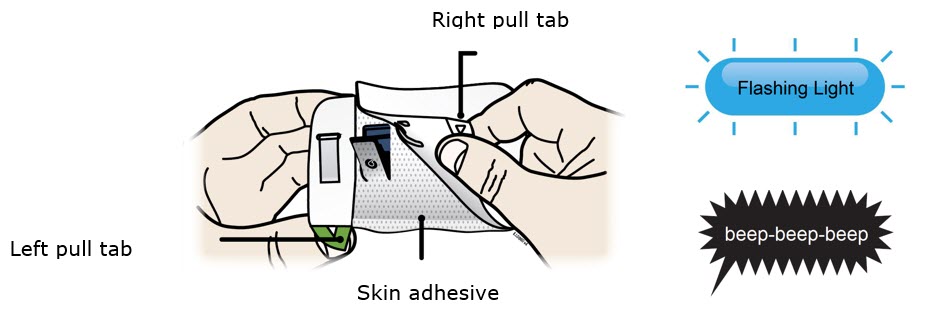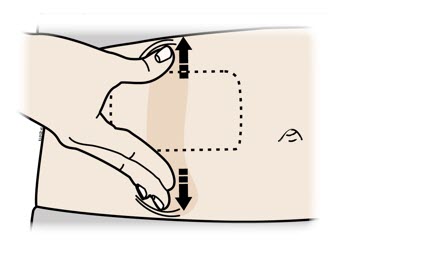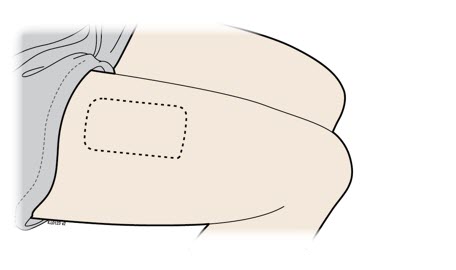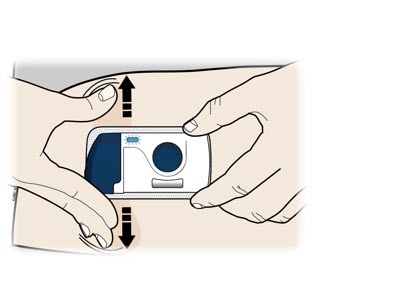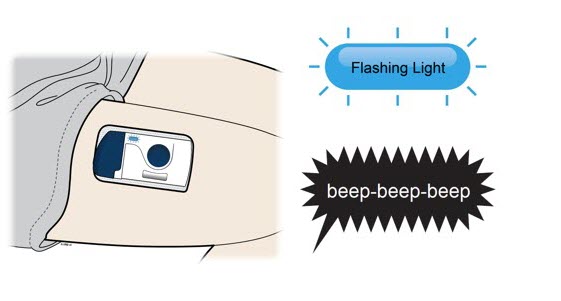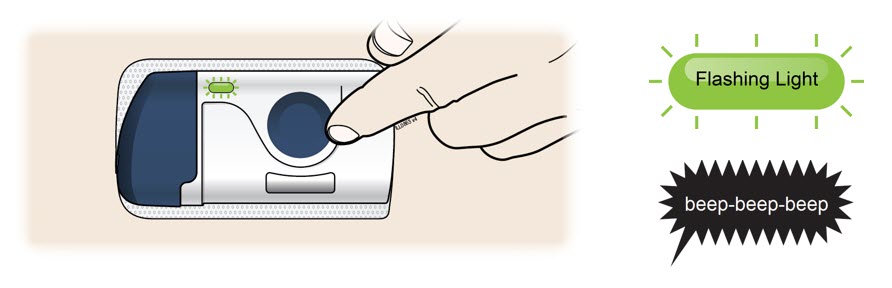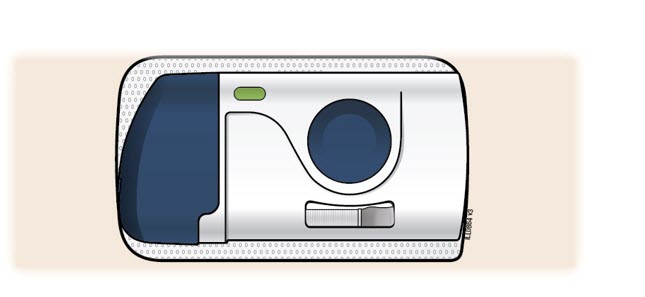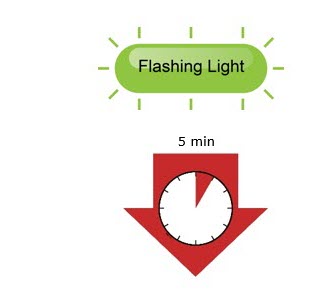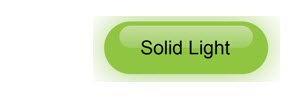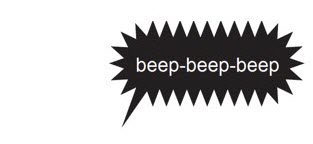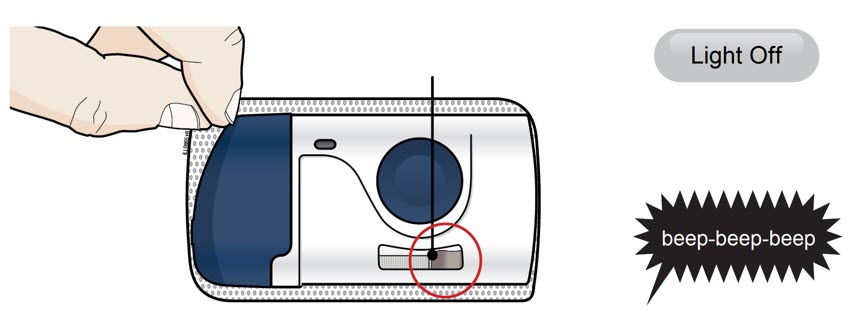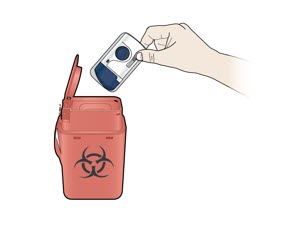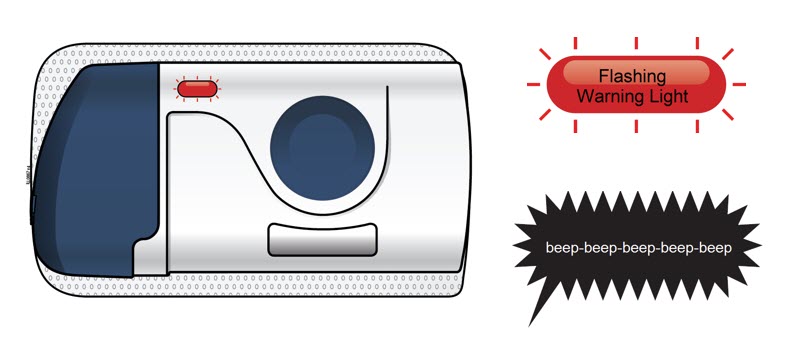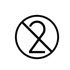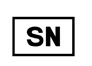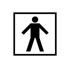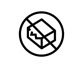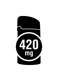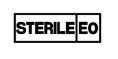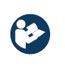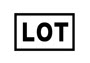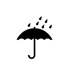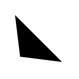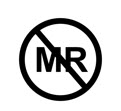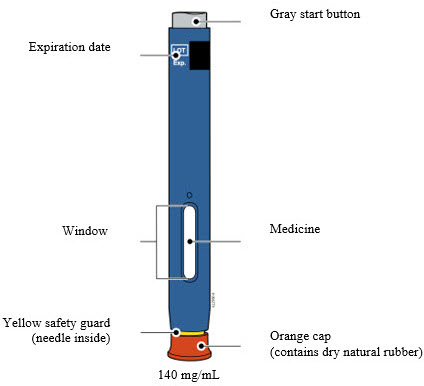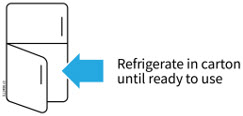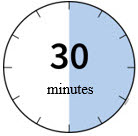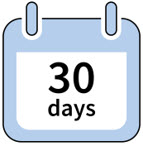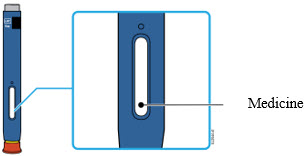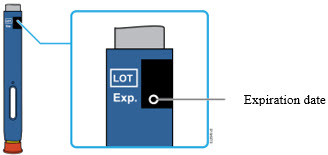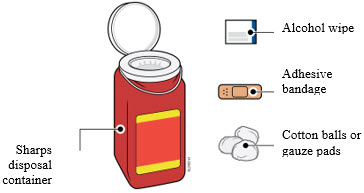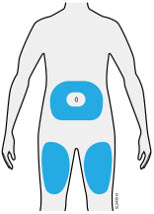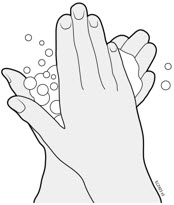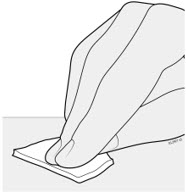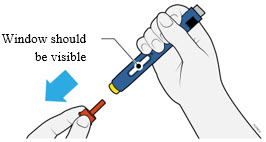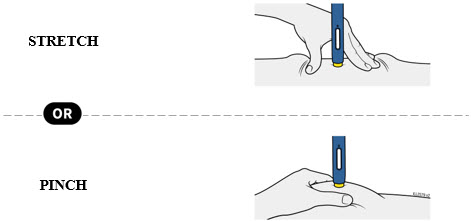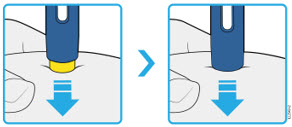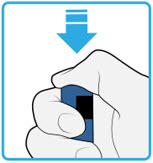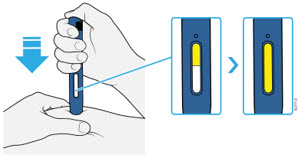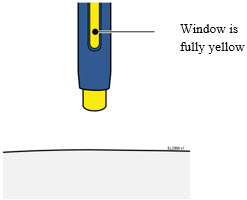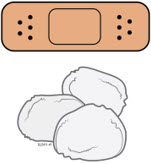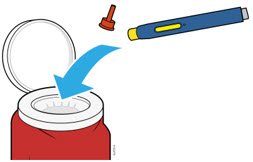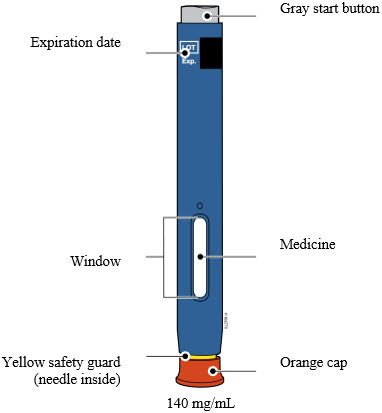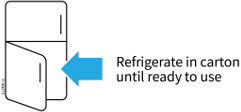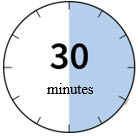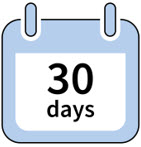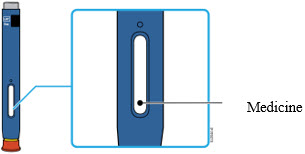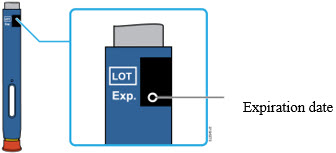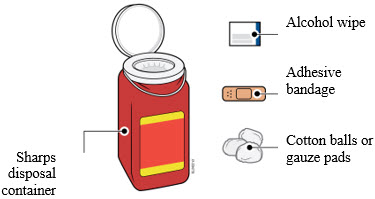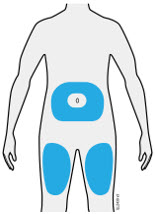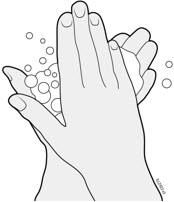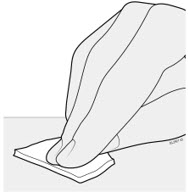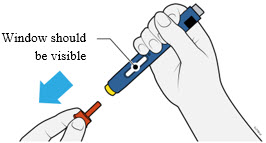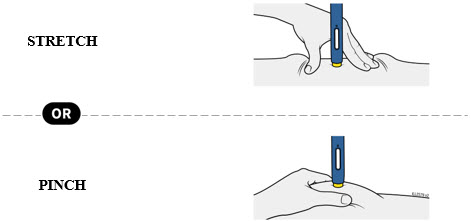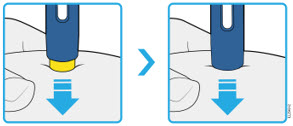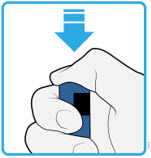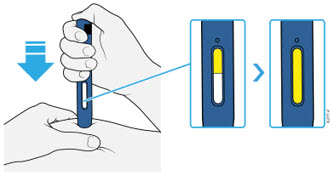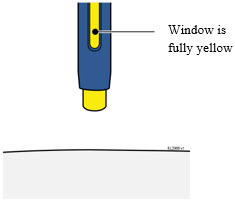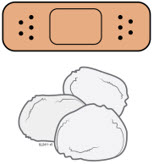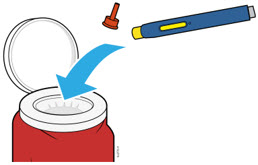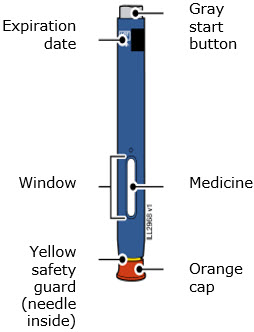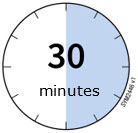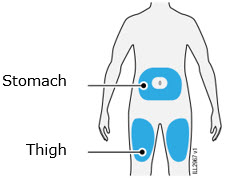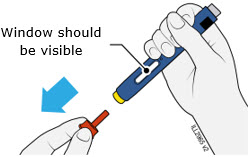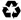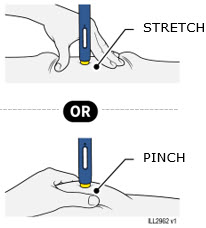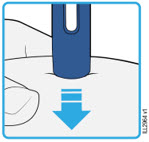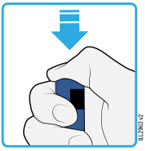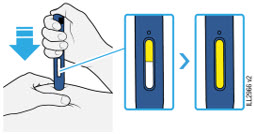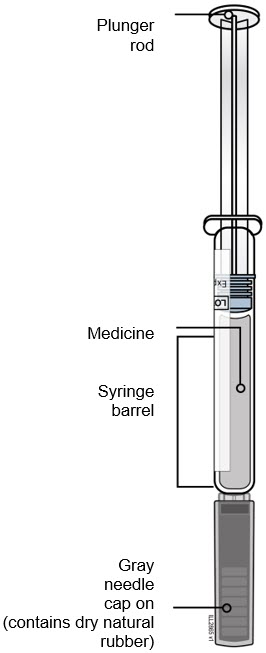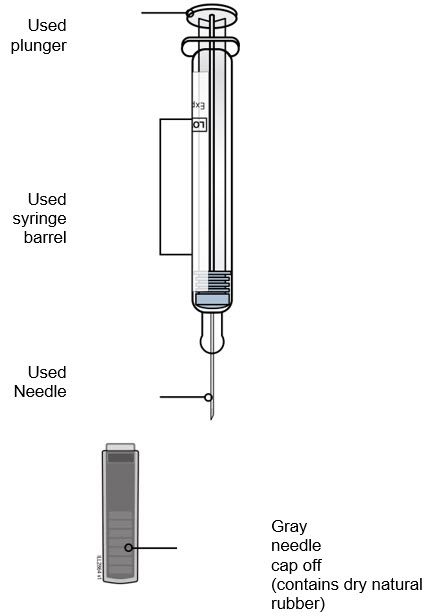 DRUG LABEL: REPATHA
NDC: 72511-760 | Form: INJECTION, SOLUTION
Manufacturer: Amgen USA Inc.
Category: prescription | Type: HUMAN PRESCRIPTION DRUG LABEL
Date: 20260122

ACTIVE INGREDIENTS: EVOLOCUMAB 140 mg/1 mL
INACTIVE INGREDIENTS: PROLINE 25 mg/1 mL; ACETATE ION 1.2 mg/1 mL; POLYSORBATE 80 0.1 mg/1 mL; SODIUM HYDROXIDE; WATER

HIGHLIGHTS OF PRESCRIBING INFORMATION

These highlights do not include all the information needed to use REPATHA® safely and effectively. See full prescribing information for REPATHA.
REPATHA (evolocumab) injection, for subcutaneous use
Initial U.S. Approval: 2015

RECENT MAJOR CHANGES

Indications and Usage (1) | 08/2025
Dosage and Administration (2.3) | 11/2024
Warnings and Precautions (5.1) | 11/2024

1 INDICATIONS AND USAGE

REPATHA is a PCSK9 (proprotein convertase subtilisin kexin type 9) inhibitor indicated:

- To reduce the risk of major adverse cardiovascular (CV) events (CV death, myocardial infarction, stroke, unstable angina requiring hospitalization, or coronary revascularization) in adults at increased risk for these events. (1)
- As an adjunct to diet and exercise to reduce low-density lipoprotein cholesterol (LDL-C) in:
  - adults with hypercholesterolemia. (1)
  - adults and pediatric patients aged 10 years and older with heterozygous familial hypercholesterolemia (HeFH). (1)
  - adults and pediatric patients aged 10 years and older with homozygous familial hypercholesterolemia (HoFH). (1)

2 DOSAGE AND ADMINISTRATION

In adults at increased risk for CV events or with hypercholesterolemia:

- The recommended dosage of REPATHA is either 140 mg every 2 weeks OR 420 mg once monthly administered subcutaneously. (2.1)
- If switching dosage regimens, administer the first dose of the new regimen on the next scheduled date of the prior regimen. (2.1)

In adults and pediatric patients aged 10 years and older with HeFH:

- The recommended dosage of REPATHA is either 140 mg every 2 weeks OR 420 mg once monthly administered subcutaneously. (2.1)
- If switching dosage regimens, administer the first dose of the new regimen on the next scheduled date of the prior regimen. (2.1)

In adults and pediatric patients aged 10 years and older with HoFH:

- The initial recommended dosage of REPATHA is 420 mg once monthly administered subcutaneously. (2.1)
- The dosage can be increased to 420 mg every 2 weeks if a clinically meaningful response is not achieved in 12 weeks. (2.1)
- Patients on lipid apheresis may initiate treatment with 420 mg every 2 weeks to correspond with their apheresis schedule. Administer REPATHA after the apheresis session is complete. (2.1)

- Assess LDL-C when clinically appropriate. The LDL-lowering effect of REPATHA may be measured as early as 4 weeks after initiation. (2.1)
- REPATHA is available as prefilled single-dose SureClick® autoinjectors and prefilled single-dose syringes that either contain dry natural rubber (a derivative of latex) in the needle cover or are not made with natural rubber latex. Consider prescribing a presentation of REPATHA that does not contain dry natural rubber for individuals that are sensitive to latex. (2.3, 16)
- Administer REPATHA subcutaneously into areas of the abdomen, thigh, or upper arm. Rotate injection sites for each administration. (2.3)
- See Full Prescribing Information for important administration instructions. (2.3)

3 DOSAGE FORMS AND STRENGTHS

- Injection: 140 mg/mL solution prefilled single-dose SureClick® autoinjector (3)
- Injection: 140 mg/mL solution prefilled single-dose syringe (3)
- Injection: 420 mg/3.5 mL solution single-dose Pushtronex® system (on-body infusor with prefilled cartridge) (3)

4 CONTRAINDICATIONS

Patients with a history of a serious hypersensitivity reaction to evolocumab or any of the excipients in REPATHA. (4)

5 WARNINGS AND PRECAUTIONS

Hypersensitivity Reactions: Angioedema has occurred. If signs or symptoms of serious hypersensitivity reactions occur, discontinue treatment with REPATHA, treat according to the standard of care, and monitor until signs and symptoms resolve. (5.1)

6 ADVERSE REACTIONS

Common (> 5% of patients treated with REPATHA and more frequently than placebo) adverse reactions in adults with:

Primary hypercholesterolemia: nasopharyngitis, upper respiratory tract infection, influenza, back pain, and injection site reactions. (6)

Established CVD: diabetes mellitus, nasopharyngitis and upper respiratory tract infection. (6)

To report SUSPECTED ADVERSE REACTIONS, contact Amgen Medical Information at 1-800-77-AMGEN (1-800-772-6436) or FDA at 1-800-FDA-1088 or www.fda.gov/medwatch.

FULL PRESCRIBING INFORMATION

1 INDICATIONS AND USAGE

REPATHA is indicated:

- To reduce the risk of major adverse cardiovascular (CV) events (CV death, myocardial infarction, stroke, unstable angina requiring hospitalization, or coronary revascularization) in adults at increased risk for these events.
- As an adjunct to diet and exercise to reduce low-density lipoprotein cholesterol (LDL-C) in:
  - adults with hypercholesterolemia.
  - adults and pediatric patients aged 10 years and older with heterozygous familial hypercholesterolemia (HeFH).
  - adults and pediatric patients aged 10 years and older with homozygous familial hypercholesterolemia (HoFH).

2 DOSAGE AND ADMINISTRATION

2.1 Recommended Dosage

- In adults at increased risk for CV events or with hypercholesterolemia:
  - The recommended dosage of REPATHA is either 140 mg every 2 weeks OR 420 mg once monthly administered subcutaneously [see Dosage and Administration (2.3)].
  - If switching dosage regimens, administer the first dose of the new regimen on the next scheduled date of the prior regimen.
- In adults and pediatric patients aged 10 years and older with HeFH:
  - The recommended dosage of REPATHA is either 140 mg every 2 weeks OR 420 mg once monthly administered subcutaneously [see Dosage and Administration (2.3)].
  - If switching dosage regimens, administer the first dose of the new regimen on the next scheduled date of the prior regimen.
- In adults and pediatric patients aged 10 years and older with HoFH:
  - The initial recommended dosage of REPATHA is 420 mg once monthly administered subcutaneously [see Dosage and Administration (2.3)].
  - The dosage can be increased to 420 mg every 2 weeks if a clinically meaningful response is not achieved in 12 weeks.
  - Patients on lipid apheresis may initiate treatment with 420 mg every 2 weeks to correspond with their apheresis schedule. Administer REPATHA after the apheresis session is complete.
- Assess LDL-C when clinically appropriate. The LDL-lowering effect of REPATHA may be measured as early as 4 weeks after initiation.
- When monitoring LDL-C for patients receiving REPATHA 420 mg once monthly, note that LDL-C can vary during the dosing interval in some patients; recommend measuring LDL-C just prior to the next scheduled dose [see Clinical Studies (14)].

2.2 Missed Doses

If a dose is missed:

- Within 7 days from the missed dose, instruct the patient to administer REPATHA and resume the patient's original schedule.
- More than 7 days after the missed dose:
  - For an every 2-week dose, instruct the patient to wait until the next dose on the original schedule.
  - For a once-monthly dose, instruct the patient to administer the dose and start a new schedule based on this date.

2.3 Important Administration Instructions

- REPATHA is available as prefilled single-dose SureClick® autoinjectors and prefilled single-dose syringes that either contain dry natural rubber (a derivative of latex) in the needle cover or are not made with natural rubber latex [see How Supplied/Storage and Handling (16)]. Consider prescribing a presentation of REPATHA that does not contain dry natural rubber for individuals that are sensitive to latex [see Warnings and Precautions (5.1)].
- Train patients and/or caregivers on how to prepare and administer REPATHA, according to the Instructions for Use and instruct them to read and follow the Instructions for Use each time they use REPATHA.
- Prior to use, allow REPATHA to warm to room temperature for at least 30 minutes for the prefilled single-dose SureClick® autoinjector or prefilled single-dose syringe and for at least 45 minutes for the on-body infusor with prefilled cartridge if REPATHA has been refrigerated [see How Supplied/Storage and Handling (16)].
- Visually inspect REPATHA prior to administration. REPATHA is a clear to opalescent, colorless to pale yellow solution. Do not use if the solution is cloudy, discolored, or contains particles.
- Administer REPATHA subcutaneously into areas of the abdomen, thigh, or upper arm that are not tender, bruised, red, or indurated. Avoid injecting into areas with scars or stretch marks. Rotate injection sites for each administration.
- The 420 mg dose of REPATHA can be administered:
  - over 5 minutes by using the single-dose on-body infusor with prefilled cartridge, or
  - by giving 3 injections consecutively within 30 minutes using the prefilled single-dose SureClick® autoinjector or prefilled single-dose syringe.

3 DOSAGE FORMS AND STRENGTHS

REPATHA is a clear to opalescent, colorless to pale yellow solution available as follows:

- Injection: 140 mg/mL solution in a prefilled single-dose SureClick® autoinjector
- Injection: 140 mg/mL solution in a prefilled single-dose syringe
- Injection: 420 mg/3.5 mL solution in a single-dose Pushtronex® system (on-body infusor with prefilled cartridge)

4 CONTRAINDICATIONS

REPATHA is contraindicated in patients with a history of a serious hypersensitivity reaction to evolocumab or any of the excipients in REPATHA. Serious hypersensitivity reactions including angioedema have occurred in patients treated with REPATHA [see Warnings and Precautions (5.1)].

5 WARNINGS AND PRECAUTIONS

5.1 Hypersensitivity Reactions

Hypersensitivity reactions, including angioedema, have been reported in patients treated with REPATHA. If signs or symptoms of serious hypersensitivity reactions occur, discontinue treatment with REPATHA, treat according to the standard of care, and monitor until signs and symptoms resolve. REPATHA is contraindicated in patients with a history of serious hypersensitivity reactions to evolocumab or any excipient in REPATHA [see Contraindications (4)].

The prefilled single-dose SureClick® autoinjector and prefilled single-dose syringe presentations of REPATHA that contain dry natural rubber (a derivative of latex) in the needle cover may cause an allergic reaction in individuals sensitive to latex. Instruct patients to inform their healthcare provider if they are sensitive to latex. Consider prescribing a presentation of REPATHA that does not contain dry natural rubber for individuals that are sensitive to latex [see How Supplied/Storage and Handling (16)].

6 ADVERSE REACTIONS

The following adverse reactions are also discussed in other sections of the label:

- Hypersensitivity Reactions [see Warnings and Precautions (5.1)]

6.1 Clinical Trials Experience

Because clinical trials are conducted under widely varying conditions, adverse reaction rates observed in the clinical trials of a drug cannot be directly compared to rates in the clinical trials of another drug and may not reflect the rates observed in clinical practice.

Adverse Reactions in Adults with Primary Hypercholesterolemia

The data described below reflect exposure to REPATHA in 8 placebo-controlled trials that included 2651 patients treated with REPATHA, including 557 exposed for 6 months and 515 exposed for 1 year (median treatment duration of 12 weeks). The mean age of the population was 57 years, 49% of the population were women, 85% White, 6% Black, 8% Asians, and 2% other races.

Adverse Reactions in a 52-Week Controlled Trial

In a 52-week, double-blind, randomized, placebo-controlled trial, 599 patients received 420 mg of REPATHA subcutaneously once monthly [see Clinical Studies (14)]. The mean age was 56 years (range: 22 to 75 years), 23% were older than 65 years, 52% women, 80% White, 8% Black, 6% Asian; 6% identified as Hispanic ethnicity. Adverse reactions reported in at least 3% of REPATHA-treated patients, and more frequently than in placebo-treated patients are shown in Table 1. Adverse reactions led to discontinuation of treatment in 2.2% of REPATHA-treated patients and 1% of placebo-treated patients. The most common adverse reaction that led to REPATHA treatment discontinuation and occurred at a rate greater than placebo was myalgia (0.3% versus 0% for REPATHA and placebo, respectively).

Table 1. Adverse Reactions Occurring in ≥ 3% of REPATHA-treated Patients and More Frequently than with Placebo in a 52-Week Trial
 | Placebo (N = 302) % | REPATHA (N = 599) %
Nasopharyngitis | 9.6 | 10.5
Upper respiratory tract infection | 6.3 | 9.3
Influenza | 6.3 | 7.5
Back pain | 5.6 | 6.2
Injection site reactions [includes erythema, pain, bruising] | 5.0 | 5.7
Cough | 3.6 | 4.5
Urinary tract infection | 3.6 | 4.5
Sinusitis | 3.0 | 4.2
Headache | 3.6 | 4.0
Myalgia | 3.0 | 4.0
Dizziness | 2.6 | 3.7
Musculoskeletal pain | 3.0 | 3.3
Hypertension | 2.3 | 3.2
Diarrhea | 2.6 | 3.0
Gastroenteritis | 2.0 | 3.0

Adverse Reactions in Seven Pooled 12-Week Controlled Trials

In seven pooled 12-week, double-blind, randomized, placebo-controlled trials, 993 patients received 140 mg of REPATHA subcutaneously every 2 weeks and 1059 patients received 420 mg of REPATHA subcutaneously monthly. The mean age was 57 years (range: 18 to 80 years), 29% were older than 65 years, 49% women, 85% White, 5% Black, 9% Asian; 5% identified as Hispanic ethnicity. Adverse reactions reported in at least 1% of REPATHA-treated patients, and more frequently than in placebo-treated patients, are shown in Table 2.

Table 2. Adverse Reactions Occurring in ≥ 1% of REPATHA-treated Patients and More Frequently than with Placebo in Pooled 12-Week Trials
 | Placebo (N = 1224) % | REPATHA [140 mg every 2 weeks and 420 mg once monthly combined] (N = 2052) %
Nasopharyngitis | 3.9 | 4.0
Back pain | 2.2 | 2.3
Upper respiratory tract infection | 2.0 | 2.1
Arthralgia | 1.6 | 1.8
Nausea | 1.2 | 1.8
Fatigue | 1.0 | 1.6
Muscle spasms | 1.2 | 1.3
Urinary tract infection | 1.2 | 1.3
Cough | 0.7 | 1.2
Influenza | 1.1 | 1.2
Contusion | 0.5 | 1.0

Adverse Reactions in Eight Pooled Controlled Trials (Seven 12-Week Trials and One 52-Week Trial)

The adverse reactions described below are from a pool of the 52-week trial and seven 12-week trials. The mean and median exposure durations of REPATHA in this pool of eight trials were 20 weeks and 12 weeks, respectively.

Local Injection Site Reactions

Injection site reactions occurred in 3.2% and 3.0% of REPATHA-treated and placebo-treated patients, respectively. The most common injection site reactions were erythema, pain, and bruising. The proportions of patients who discontinued treatment due to local injection site reactions in REPATHA-treated patients and placebo-treated patients were 0.1% and 0%, respectively.

Hypersensitivity Reactions

Hypersensitivity reactions occurred in 5.1% and 4.7% of REPATHA-treated and placebo-treated patients, respectively. The most common hypersensitivity reactions were rash (1.0% versus 0.5% for REPATHA and placebo, respectively), eczema (0.4% versus 0.2%), erythema (0.4% versus 0.2%), and urticaria (0.4% versus 0.1%).

Adverse Reactions in the Cardiovascular Outcomes Trial

In a double-blind, randomized, placebo-controlled cardiovascular outcomes trial, 27,525 patients received at least one dose of REPATHA or placebo [see Clinical Studies (14)]. The mean age was 62.5 years (range: 40 to 86 years), 45% were 65 years or older, 9% were 75 years or older, 25% women, 85% White, 2% Black and 10% Asian; 8% identified as Hispanic ethnicity. Patients were exposed to REPATHA or placebo for a median of 24.8 months; 91% of patients were exposed for ≥ 12 months, 54% were exposed for ≥ 24 months and 5% were exposed for ≥ 36 months.

The safety profile of REPATHA in this trial was generally consistent with the safety profile described above in the 12- and 52-week controlled trials involving patients with primary hypercholesterolemia. Common adverse reactions (> 5% of patients treated with REPATHA and occurring more frequently than placebo) included diabetes mellitus (8.8% REPATHA, 8.2% placebo), nasopharyngitis (7.8% REPATHA, 7.4% placebo), and upper respiratory tract infection (5.1% REPATHA, 4.8% placebo).

Among the 16,676 patients without diabetes mellitus at baseline, the incidence of new-onset diabetes mellitus during the trial was 8.1% in patients treated with REPATHA compared with 7.7% in patients that received placebo.

Adverse Reactions in Pediatric Patients with HeFH

In a 24-week, randomized, placebo-controlled, double-blind trial of 157 pediatric patients with HeFH, 104 patients received 420 mg REPATHA subcutaneously once monthly [see Clinical Studies (14)]. The mean age was 13.7 years (range: 10 to 17 years), 56% were female, 85% White, 1% Black, 1% Asian, and 13% other; 8% identified as Hispanic ethnicity. Common adverse reactions (> 5% of patients treated with REPATHA and occurring more frequently than placebo) included:

- Nasopharyngitis (12% versus 11%)
- Headache (11% versus 2%)
- Oropharyngeal pain (7% versus 0%)
- Influenza (6% versus 4%)
- Upper respiratory tract infection (6% versus 2%)

Adverse Reactions in Adults and Pediatric Patients with HoFH

In a 12-week, double-blind, randomized, placebo-controlled trial of 49 patients with HoFH, 33 patients received 420 mg of REPATHA subcutaneously once monthly [see Clinical Studies (14)]. The mean age was 31 years (range: 13 to 57 years), 49% were women, 90% White, 4% Asian, and 6% other. The adverse reactions that occurred in at least two (6.1%) REPATHA-treated patients, and more frequently than in placebo-treated patients, included:

- Upper respiratory tract infection (9.1% versus 6.3%)
- Influenza (9.1% versus 0%)
- Gastroenteritis (6.1% versus 0%)
- Nasopharyngitis (6.1% versus 0%)

In a multicenter, open-label 5-year extension study, 106 patients with HoFH, including 14 pediatric patients, received 420 mg of REPATHA subcutaneously once monthly or every 2 weeks [see Clinical Studies (14)]. The mean age was 34 years (range: 13 to 68 years), 51% were women, 80% White, 12% Asian, 1% Native American, and 7% other; 5% identified as Hispanic ethnicity. No new adverse reactions were observed during the open-label extension study.

6.2 Immunogenicity

As with all therapeutic proteins, there is potential for immunogenicity. The detection of antibody formation is highly dependent on the sensitivity and specificity of the assay. Additionally, the observed incidence of antibody (including neutralizing antibody) positivity in an assay may be influenced by several factors including assay methodology, sample handling, timing of sample collection, concomitant medications, and underlying disease. For these reasons, comparison of the incidence of antibodies to REPATHA in the studies described below with the incidence of antibodies in other studies or to other products may be misleading.

The immunogenicity of REPATHA has been evaluated using an electrochemiluminescent bridging screening immunoassay for the detection of binding anti-drug antibodies. For patients whose sera tested positive in the screening immunoassay, an in vitro biological assay was performed to detect neutralizing antibodies.

In a pool of placebo- and active-controlled clinical trials, 0.3% (48 out of 17,992) of adult patients treated with at least one dose of REPATHA tested positive for the development of binding antibodies. Patients whose sera tested positive for binding antibodies were further evaluated for neutralizing antibodies; none of the patients tested positive for neutralizing antibodies.

The development of anti-evolocumab antibodies was not detected in clinical trials of pediatric patients treated with REPATHA.

There was no evidence that the presence of anti-drug binding antibodies impacted the pharmacokinetic profile, clinical response, or safety of REPATHA.

6.3 Postmarketing Experience

The following additional adverse reactions have been identified during post-approval use of REPATHA. Because these reactions are reported voluntarily from a population of uncertain size, it is not always possible to reliably estimate their frequency or establish a causal relationship to drug exposure.

- Hypersensitivity reactions: Angioedema
- Influenza-like illness

8 USE IN SPECIFIC POPULATIONS

8.1 Pregnancy

Risk Summary

Available data from clinical trials and postmarketing reports on REPATHA use in pregnant women are insufficient to evaluate for a drug-associated risk of major birth defects, miscarriage or other adverse maternal or fetal outcomes. In animal reproduction studies, there were no effects on pregnancy or neonatal/infant development when monkeys were subcutaneously administered evolocumab from organogenesis through parturition at dose exposures up to 12 times the exposure at the maximum recommended human dose of 420 mg every month. In a similar study with another drug in the PCSK9 inhibitor antibody class, humoral immune suppression was observed in infant monkeys exposed to that drug in utero at all doses. The exposures where immune suppression occurred in infant monkeys were greater than those expected clinically. No assessment for immune suppression was conducted with evolocumab in infant monkeys. Measurable evolocumab serum concentrations were observed in the infant monkeys at birth at comparable levels to maternal serum, indicating that evolocumab, like other IgG antibodies, crosses the placental barrier. Monoclonal antibodies are transported across the placenta in increasing amounts especially near term; therefore, evolocumab has the potential to be transmitted from the mother to the developing fetus.

The estimated background risk of major birth defects and miscarriage for the indicated population(s) is unknown. In the U.S. general population, the estimated background risk of major birth defects and miscarriage in clinically recognized pregnancies is 2-4% and 15-20%, respectively.

There is a pregnancy safety study for REPATHA. If REPATHA is administered during pregnancy, healthcare providers should report REPATHA exposure by contacting Amgen at 1-800-77-AMGEN (1-800-772-6436) or https://wwwext.amgen.com/products/global-patient-safety/adverse-event-reporting.

Data

Animal Data

In cynomolgus monkeys, no effects on embryo-fetal or postnatal development (up to 6 months of age) were observed when evolocumab was dosed during organogenesis to parturition at 50 mg/kg once every 2 weeks by the subcutaneous route at exposures 30- and 12-fold the recommended human doses of 140 mg every 2 weeks and 420 mg once monthly, respectively, based on plasma AUC. No test of humoral immunity in infant monkeys was conducted with evolocumab.

8.2 Lactation

Risk Summary

There is no information regarding the presence of evolocumab in human milk, the effects on the breastfed infant, or the effects on milk production. Human IgG is present in human milk, but published data suggest that breast milk antibodies do not enter the neonatal and infant circulation in substantial amounts.

The development and health benefits of breastfeeding should be considered along with the mother's clinical need for REPATHA and any potential adverse effects on the breastfed infant from REPATHA or from the underlying maternal condition.

8.4 Pediatric Use

The safety and effectiveness of REPATHA in combination with diet and other LDL-C-lowering therapies for the treatment of HoFH have been established in pediatric patients aged 10 years and older. Use of REPATHA for this indication is supported by evidence from an adequate and well-controlled trial in adults and pediatric patients aged 13 years and older with HoFH (including 7 pediatric patients treated with REPATHA) and from open-label studies which included an additional 19 pediatric patients aged 11 years and older with HoFH not previously treated with REPATHA [see Adverse Reactions (6.1) and Clinical Studies (14)].

The safety and effectiveness of REPATHA as an adjunct to diet and other LDL-C-lowering therapies for the treatment of HeFH have been established in pediatric patients aged 10 years and older. Use of REPATHA for this indication is based on data from a 24-week, randomized, placebo-controlled, double-blind trial in pediatric patients with HeFH. In the trial, 104 patients received REPATHA 420 mg subcutaneously once monthly and 53 patients received placebo; 39 patients (25%) were 10 to 11 years of age [see Adverse Reactions (6.1) and Clinical Studies (14)].

The safety and effectiveness of REPATHA have not been established in pediatric patients with HeFH or HoFH who are younger than 10 years old or in pediatric patients with other types of hypercholesterolemia.

8.5 Geriatric Use

In controlled trials, 7656 (41%) patients treated with REPATHA were ≥ 65 years old and 1500 (8%) were ≥ 75 years old. No overall differences in safety or effectiveness were observed between these patients and younger patients, and other reported clinical experience has not identified differences in responses between the elderly and younger patients, but greater sensitivity of some older individuals cannot be ruled out.

8.6 Renal Impairment

No dose adjustment is needed in patients with renal impairment [see Clinical Pharmacology (12.3)].

8.7 Hepatic Impairment

No dose adjustment is needed in patients with mild to moderate hepatic impairment (Child-Pugh A or B). No data are available in patients with severe hepatic impairment [see Clinical Pharmacology (12.3)].

11 DESCRIPTION

Evolocumab is a human monoclonal immunoglobulin G2 (IgG2) directed against human proprotein convertase subtilisin kexin type 9 (PCSK9). Evolocumab has an approximate molecular weight (MW) of 144 kDa and is produced in genetically engineered mammalian (Chinese hamster ovary) cells.

REPATHA is a sterile, preservative-free, clear to opalescent, colorless to pale yellow solution for subcutaneous use. Each 1 mL prefilled single-dose SureClick® autoinjector and prefilled single-dose syringe contains 140 mg evolocumab, acetate (1.2 mg), polysorbate 80 (0.1 mg), proline (25 mg) in Water for Injection, USP. Sodium hydroxide may be used to adjust to a pH of 5.0. Each single-dose Pushtronex® system (on-body infusor with prefilled cartridge) delivers a 3.5 mL solution containing 420 mg evolocumab, acetate (4.2 mg), polysorbate 80 (0.35 mg), proline (89 mg) in Water for Injection, USP. Sodium hydroxide may be used to adjust to a pH of 5.0.

12 CLINICAL PHARMACOLOGY

12.1 Mechanism of Action

Evolocumab is a human monoclonal IgG2 directed against human proprotein convertase subtilisin kexin type 9 (PCSK9). PCSK9 binds to the low-density lipoprotein receptor (LDLR) on the surface of hepatocytes to promote LDLR degradation within the liver. By inhibiting the binding of PCSK9 to LDLR, evolocumab increases the number of LDLRs available to clear LDL from the blood, thereby lowering LDL-C levels.

12.2 Pharmacodynamics

Following single subcutaneous administration of 140 mg or 420 mg of evolocumab, maximum suppression of circulating unbound PCSK9 occurred by 4 hours. Unbound PCSK9 concentrations returned toward baseline when evolocumab concentrations decreased below the limit of quantitation. Maximum LDL-C reduction occurred by 2 weeks after a single-dose of 140 mg of evolocumab and by 3 weeks after a single-dose of 420 mg of evolocumab.

12.3 Pharmacokinetics

Evolocumab exhibits non-linear kinetics as a result of binding to PCSK9. Administration of the 140 mg dose in healthy volunteers resulted in a Cmax mean of 18.6 µg/mL and AUClast mean of 188 day∙µg/mL. Administration of the 420 mg dose in healthy volunteers resulted in a Cmax mean of 59.0 µg/mL and AUClast mean of 924 day∙µg/mL. Following a single 420 mg intravenous dose, the mean systemic clearance was estimated to be 12 mL/hr. An approximate 2- to 3-fold accumulation was observed in trough serum concentrations (Cmin 7.21) following 140 mg doses administered subcutaneously every 2 weeks or following 420 mg doses administered subcutaneously monthly (Cmin 11.2), and serum trough concentrations approached steady-state by 12 weeks of dosing.

Absorption

Following a single subcutaneous dose of 140 mg or 420 mg evolocumab administered to healthy adults, median peak serum concentrations were attained in 3 to 4 days, and estimated absolute bioavailability was 72%.

Distribution

Following a single 420 mg intravenous dose, the mean steady-state volume of distribution was estimated to be 3.3 L.

Elimination

Two elimination phases were observed for REPATHA. At low concentrations, the elimination is predominately through saturable binding to target (PCSK9), while at higher concentrations the elimination of REPATHA is largely through a non-saturable proteolytic pathway. REPATHA was estimated to have an effective half-life of 11 to 17 days.

Specific Populations

The pharmacokinetics of evolocumab were not affected by age, gender, race, or creatinine clearance across all approved populations [see Use in Specific Populations (8.5)].

The exposure of evolocumab decreased with increasing body weight. These differences are not clinically meaningful.

Pediatric Patients

The pharmacokinetics of REPATHA were evaluated in 103 pediatric patients aged 10 to 17 years with HeFH (Study 6) [see Use in Specific Populations (8.4), and Clinical Studies (14)]. Following subcutaneous administration of 420 mg REPATHA once monthly, mean trough serum concentrations were 22.4 mcg/mL and 25.8 mcg/mL over the Week 12 and Week 24 time points, respectively. The pharmacokinetics of REPATHA were evaluated in 12 pediatric patients aged 11 to 17 years with HoFH (Study 9) [see Use in Specific Populations (8.4), and Clinical Studies (14)]. Following subcutaneous administration of 420 mg REPATHA once monthly, mean serum trough concentrations were 20.3 mcg/mL and 17.6 mcg/mL at Week 12 and Week 80, respectively.

Renal Impairment

Since monoclonal antibodies are not known to be eliminated via renal pathways, renal function is not expected to impact the pharmacokinetics of evolocumab.

In a clinical trial of 18 patients with either normal renal function (estimated glomerular filtration rate [eGFR] ≥ 90 mL/min/1.73 m^2, n = 6), severe renal impairment (eGFR < 30 mL/min/1.73 m^2, n = 6), or end-stage renal disease (ESRD) receiving hemodialysis (n = 6), exposure to evolocumab after a single 140 mg subcutaneous dose was decreased in patients with severe renal impairment or ESRD receiving hemodialysis. Reductions in PCSK9 levels in patients with severe renal impairment or ESRD receiving hemodialysis was similar to those with normal renal function [see Use in Specific Populations (8.6)].

Hepatic Impairment

Following a single 140 mg subcutaneous dose of evolocumab in patients with mild or moderate hepatic impairment, a 20-30% lower mean Cmax and 40-50% lower mean AUC were observed as compared to healthy patients [see Use in Specific Populations (8.7)].

Drug Interaction Studies

An approximately 20% decrease in the Cmax and AUC of evolocumab was observed in adult patients co-administered with a high-intensity statin regimen. This difference is not clinically meaningful.

13 NONCLINICAL TOXICOLOGY

13.1 Carcinogenesis, Mutagenesis, Impairment of Fertility

The carcinogenic potential of evolocumab was evaluated in a lifetime study conducted in the hamster at dose levels of 10, 30, and 100 mg/kg administered every 2 weeks. There were no evolocumab-related tumors at the highest dose at systemic exposures up to 38- and 15-fold the recommended human doses of 140 mg every 2 weeks and 420 mg once monthly, respectively, based on plasma AUC. The mutagenic potential of evolocumab has not been evaluated; however, monoclonal antibodies are not expected to alter DNA or chromosomes.

There were no adverse effects on fertility (including estrous cycling, sperm analysis, mating performance, and embryonic development) at the highest dose in a fertility and early embryonic developmental toxicology study in hamsters when evolocumab was subcutaneously administered at 10, 30, and 100 mg/kg every 2 weeks. The highest dose tested corresponds to systemic exposures up to 30- and 12-fold the recommended human doses of 140 mg every 2 weeks and 420 mg once monthly, respectively, based on plasma AUC. In addition, there were no adverse evolocumab-related effects on surrogate markers of fertility (reproductive organ histopathology, menstrual cycling, or sperm parameters) in a 6-month chronic toxicology study in sexually mature monkeys subcutaneously administered evolocumab at 3, 30, and 300 mg/kg once weekly. The highest dose tested corresponds to 744- and 300-fold the recommended human doses of 140 mg every 2 weeks and 420 mg once monthly, respectively, based on plasma AUC.

13.2 Animal Toxicology and/or Pharmacology

During a 3-month toxicology study of 10 and 100 mg/kg once every 2 weeks evolocumab in combination with 5 mg/kg once daily rosuvastatin in adult monkeys, there were no effects of evolocumab on the humoral immune response to keyhole limpet hemocyanin (KLH) after 1 to 2 months exposure. The highest dose tested corresponds to exposures 54- and 21-fold higher than the recommended human doses of 140 mg every 2 weeks and 420 mg once monthly, respectively, based on plasma AUC. Similarly, there were no effects of evolocumab on the humoral immune response to KLH (after 3 to 4 months exposure) in a 6-month study in cynomolgus monkeys at dose levels up to 300 mg/kg once weekly evolocumab corresponding to exposures 744- and 300-fold greater than the recommended human doses of 140 mg every 2 weeks and 420 mg once monthly, respectively, based on plasma AUC.

14 CLINICAL STUDIES

Adult Patients with Established Cardiovascular Disease

Study 1 (FOURIER, NCT01764633) was a double-blind, randomized, placebo-controlled, event-driven trial in 27,564 (13,784 REPATHA, 13,780 placebo) adult patients with established cardiovascular disease and with LDL-C ≥ 70 mg/dL and/or non-HDL-C ≥ 100 mg/dL despite high- or moderate-intensity statin therapy. Patients were randomly assigned 1:1 to receive either subcutaneous injections of REPATHA (140 mg every 2 weeks or 420 mg once monthly) or placebo; 86% used the every-2-week regimen throughout the trial. The median follow-up duration was 26 months. Overall, 99.2% of patients were followed until the end of the trial or death.

The mean (SD) age at baseline was 63 (9) years, with 45% being at least 65 years old; 25% were women. The trial population was 85% White, 2% Black, and 10% Asian; 8% identified as Hispanic ethnicity. Regarding prior diagnoses of cardiovascular disease, 81% had prior myocardial infarction, 19% prior non-hemorrhagic stroke, and 13% had symptomatic peripheral arterial disease. Selected additional baseline risk factors included hypertension (80%), diabetes mellitus (1% type 1; 36% type 2), current daily cigarette smoking (28%), New York Heart Association class I or II congestive heart failure (23%), and eGFR < 60 mL/min per 1.73 m^2 (6%). Most patients were on a high- (69%) or moderate-intensity (30%) statin therapy at baseline, and 5% were also taking ezetimibe. Most patients were taking at least one other cardiovascular medication including anti-platelet agents (93%), beta blockers (76%), angiotensin converting enzyme (ACE) inhibitors (56%), or angiotensin receptor blockers (23%). On stable background lipid-lowering therapy, the median [Q1, Q3] LDL-C at baseline was 92 [80, 109] mg/dL; the mean (SD) was 98 (28) mg/dL.

REPATHA significantly reduced the risk for the primary composite endpoint (time to first occurrence of cardiovascular death, myocardial infarction, stroke, hospitalization for unstable angina, or coronary revascularization; p < 0.0001) and the key secondary composite endpoint (time to first occurrence of cardiovascular death, myocardial infarction, or stroke; p < 0.0001). The Kaplan-Meier estimates of the cumulative incidence of the primary and key secondary composite endpoints over time are shown in Figure 1 and Figure 2 below.

The results of primary and secondary efficacy endpoints are shown in Table 3 below.

Table 3. Effect of REPATHA on Cardiovascular Events in Patients with Established Cardiovascular Disease in FOURIER
 | Placebo |  | REPATHA |  | REPATHA vs. Placebo
 | N = 13780 n (%) | Incidence Rate (per 100 patient years) | N = 13784 n (%) | Incidence Rate (per 100 patient years) | Hazard Ratio (95% CI)
Primary composite endpoint
Time to first occurrence of cardiovascular death, myocardial infarction, stroke, coronary revascularization, hospitalization for unstable angina | 1563 (11.3) | 5.2 | 1344 (9.8) | 4.5 | 0.85 (0.79, 0.92)
Key secondary composite endpoint
Time to first occurrence of cardiovascular death, myocardial infarction, stroke | 1013 (7.4) | 3.4 | 816 (5.9) | 2.7 | 0.80 (0.73, 0.88)
Other secondary endpoints
Time to cardiovascular death | 240 (1.7) | 0.8 | 251 (1.8) | 0.8 | 1.05 (0.88, 1.25)
Time to death by any cause [Time to death by any cause is not a component of either the primary composite endpoint or key secondary composite endpoint.] | 426 (3.1) | 1.4 | 444 (3.2) | 1.5 | 1.04 (0.91, 1.19)
Time to first fatal or non-fatal myocardial infarction | 639 (4.6) | 2.1 | 468 (3.4) | 1.6 | 0.73 (0.65, 0.82)
Time to first fatal or non-fatal stroke | 262 (1.9) | 0.9 | 207 (1.5) | 0.7 | 0.79 (0.66, 0.95)
Time to first coronary revascularization | 965 (7.0) | 3.2 | 759 (5.5) | 2.5 | 0.78 (0.71, 0.86)
Time to first hospitalization for unstable angina [Not a prespecified endpoint; an ad hoc analysis was performed to ensure results are provided for each individual component of the primary endpoint.] | 239 (1.7) | 0.8 | 236 (1.7) | 0.8 | 0.99 (0.82, 1.18)

Figure 1. Estimated Cumulative Incidence of Primary Composite Endpoint Over 3 Years in FOURIER

Figure 2. Estimated Cumulative Incidence of Key Secondary Composite Endpoint Over 3 Years in FOURIER

The difference between REPATHA and placebo in mean percent change in LDL-C from baseline to Week 12 was −63% (95% CI: −63%, −62%) and from baseline to Week 72 was −57% (95% CI: −58%, −56%). At Week 48, the median [Q1, Q3] LDL-C was 26 [15, 46] mg/dL in the REPATHA group, with 47% of patients having LDL-C < 25 mg/dL.

In EBBINGHAUS (NCT02207634), a substudy of 1974 patients enrolled in the FOURIER trial, REPATHA was non-inferior to placebo on selected cognitive function domains as assessed with the use of neuropsychological function tests over a median follow-up of 19 months.

Primary Hypercholesterolemia

Study 2 (LAPLACE-2, NCT01763866) was a multicenter, double-blind, randomized controlled 12-week trial in which patients were initially randomized to an open-label specific statin regimen for a 4-week lipid stabilization period followed by random assignment to subcutaneous injections of REPATHA 140 mg every 2 weeks, REPATHA 420 mg once monthly, or placebo for 12 weeks. The trial included 1896 patients with hypercholesterolemia who received REPATHA, placebo, or ezetimibe as add-on therapy to daily doses of statins (atorvastatin, rosuvastatin, or simvastatin). Ezetimibe was also included as an active control only among those assigned to background atorvastatin. Overall, the mean age at baseline was 60 years (range: 20 to 80 years), 35% were ≥ 65 years old, 46% women, 94% White, 4% were Black, and 1% Asian; 5% identified as Hispanic or Latino ethnicity. After 4 weeks of background statin therapy, the mean baseline LDL-C ranged between 77 and 127 mg/dL across the five background therapy arms.

The difference between REPATHA and placebo in mean percent change in LDL-C from baseline to Week 12 was −71% (95% CI: −74%, −67%; p < 0.0001) and −63% (95% CI: −68%, −57%; p < 0.0001) for the 140 mg every 2 weeks and 420 mg once monthly dosages, respectively. The difference between REPATHA and ezetimibe in mean percent change in LDL-C from baseline to Week 12 was −45% (95% CI: −52%, −39%; p < 0.0001) and −41% (95% CI: −47%, −35%; p < 0.0001) for the 140 mg every 2 weeks and 420 mg once monthly dosages, respectively. For additional results, see Table 4 and Figure 3.

Table 4. Effect of REPATHA on Lipid Parameters in Patients with Hypercholesterolemia on Background Statin Regimens (Mean % Change from Baseline to Week 12 in LAPLACE-2)
Treatment Group | LDL-C | Non-HDL-C | Apo B | Total Cholesterol
REPATHA every 2 weeks vs. Placebo every 2 weeks
(Background statin: atorvastatin 10 mg or 80 mg; rosuvastatin 5 mg or 40 mg; simvastatin 40 mg)
Placebo every 2 weeks (n = 281) | 8 | 6 | 5 | 4
REPATHA 140 mg every 2 weeks [140 mg every 2 weeks or 420 mg once monthly yield similar reductions in LDL-C] (n = 555) | -63 | -53 | -49 | -36
Mean difference from placebo (95% CI) | -71 (-74, -67) | -59 (-62, -55) | -55 (-58, -52) | -40 (-43, -38)
REPATHA once monthly vs. Placebo once monthly
(Background statin: atorvastatin 10 mg or 80 mg; rosuvastatin 5 mg or 40 mg; simvastatin 40 mg)
Placebo once monthly (n = 277) | 4 | 5 | 3 | 2
REPATHA 420 mg once monthly (n = 562) | -59 | -50 | -46 | -34
Mean difference from placebo (95% CI) | -63 (-68, -57) | -54 (-58, -50) | -50 (-53, -47) | -36 (-39, -33)
REPATHA every 2 weeks vs. Ezetimibe 10 mg daily
(Background statin: atorvastatin 10 mg or 80 mg)
Ezetimibe 10 mg daily (n = 112) | -17 | -16 | -14 | -12
REPATHA 140 mg every 2 weeks (n = 219) | -63 | -52 | -49 | -36
Mean difference from Ezetimibe (95% CI) | -45 (-52, -39) | -36 (-41, -31) | -35 (-40, -31) | -24 (-28, -20)
REPATHA once monthly vs. Ezetimibe 10 mg daily
(Background statin: atorvastatin 10 mg or 80 mg)
Ezetimibe 10 mg daily (n = 109) | -19 | -16 | -11 | -12
REPATHA 420 mg once monthly (n = 220) | -59 | -50 | -46 | -34
Mean difference from Ezetimibe (95% CI) | -41 (-47, -35) | -35 (-40, -29) | -34 (-39, -30) | -22 (-26, -19)
Estimates based on a multiple imputation model that accounts for treatment adherence

Figure 3. Effect of REPATHA on LDL-C in Patients with Hypercholesterolemia when Combined with Statins (Mean % Change from Baseline to Week 12 in LAPLACE-2)

Estimates based on a multiple imputation model that accounts for treatment adherence

Error bars indicate 95% confidence intervals

Study 3 (DESCARTES, NCT01516879) was a multicenter, double-blind, randomized, placebo-controlled, 52-week trial that included 901 patients with hypercholesterolemia who received protocol-determined background lipid-lowering therapy of a cholesterol-lowering diet either alone or in addition to atorvastatin (10 mg or 80 mg daily) or the combination of atorvastatin 80 mg daily with ezetimibe. After stabilization on background therapy, patients were randomly assigned to the addition of placebo or REPATHA 420 mg administered subcutaneously once monthly. Overall, the mean age at baseline was 56 years (range: 25 to 75 years), 23% were ≥ 65 years, 52% women, 80% White, 8% Black, and 6% Asian; 6% identified as Hispanic or Latino ethnicity. After stabilization on the assigned background therapy, the mean baseline LDL-C ranged between 90 and 117 mg/dL across the four background therapy groups.

In these patients with hypercholesterolemia on a protocol-determined background therapy, the difference between REPATHA 420 mg once monthly and placebo in mean percent change in LDL-C from baseline to Week 52 was −55% (95% CI: −60%, −50%; p < 0.0001) (Table 5 and Figure 4). For additional results, see Table 5.

Table 5. Effect of REPATHA on Lipid Parameters in Patients with Hypercholesterolemia [Prior to randomization, patients were stabilized on background therapy consisting of a cholesterol-lowering diet either alone or in addition to atorvastatin (10 mg or 80 mg daily) or the combination of atorvastatin 80 mg daily with ezetimibe.] (Mean % Change from Baseline to Week 52 in DESCARTES)
Treatment Group | LDL-C | Non-HDL-C | Apo B | Total Cholesterol
Placebo once monthly (n = 302) | 8 | 8 | 2 | 5
REPATHA 420 mg once monthly (n = 599) | -47 | -39 | -38 | -26
Mean difference from placebo (95% CI) | -55 (-60, -50) | -46 (-50, -42) | -40 (-44, -37) | -31 (-34, -28)
Estimates based on a multiple imputation model that accounts for treatment adherence

Figure 4. Effect of REPATHA 420 mg Once Monthly on LDL-C in Patients with Hypercholesterolemia in DESCARTES

Estimates based on a multiple imputation model that accounts for treatment adherence

Error bars indicate 95% confidence intervals

Study 4 (MENDEL-2, NCT01763827) was a multicenter, double-blind, randomized, placebo- and active-controlled, 12-week trial that included 614 patients with hypercholesterolemia who were not taking lipid-lowering therapy at baseline. Patients were randomly assigned to receive subcutaneous injections of REPATHA 140 mg every 2 weeks, REPATHA 420 mg once monthly, or placebo for 12 weeks. Blinded administration of ezetimibe was also included as an active control. Overall, the mean age at baseline was 53 years (range: 20 to 80 years), 18% were ≥ 65 years old, 66% were women, 83% White, 7% Black, and 9% Asian; 11% identified as Hispanic or Latino ethnicity. The mean baseline LDL-C was 143 mg/dL.

The difference between REPATHA and placebo in mean percent change in LDL-C from baseline to Week 12 was −55% (95% CI: −60%, −50%; p < 0.0001) and −57% (95% CI: −61%, −52%; p < 0.0001) for the 140 mg every 2 weeks and 420 mg once monthly dosages, respectively. The difference between REPATHA and ezetimibe in mean percent change in LDL-C from baseline to Week 12 was −37% (95% CI: −42%, −32%; p < 0.0001) and −38% (95% CI: −42%, −34%; p < 0.0001) for the 140 mg every 2 weeks and 420 mg once monthly dosages, respectively. For additional results, see Table 6.

Table 6. Effect of REPATHA on Lipid Parameters in Patients with Hypercholesterolemia (Mean % Change from Baseline to Week 12 in MENDEL-2)
Treatment Group | LDL-C | Non-HDL-C | Apo B | Total Cholesterol
Placebo every 2 weeks (n = 76) | 1 | 0 | 1 | 0
Ezetimibe 10 mg daily (n = 77) | -17 | -14 | -13 | -10
REPATHA 140 mg every 2 weeks [140 mg every 2 weeks or 420 mg once monthly yield similar reductions in LDL-C] (n = 153) | -54 | -47 | -44 | -34
Mean difference from placebo (95% CI) | -55 (-60, -50) | -47 (-52, -43) | -45 (-50, -41) | -34 (-37, -30)
Mean difference from Ezetimibe (95% CI) | -37 (-42, -32) | -33 (-37, -29) | -32 (-36, -27) | -23 (-27, -20)
Placebo once monthly (n = 78) | 1 | 2 | 2 | 0
Ezetimibe 10 mg daily (n = 77) | -18 | -16 | -13 | -12
REPATHA 420 mg once monthly (n = 153) | -56 | -49 | -46 | -35
Mean difference from placebo (95% CI) | -57 (-61, -52) | -51 (-54, -47) | -48 (-52, -44) | -35 (-38, -32)
Mean difference from Ezetimibe (95% CI) | -38 (-42, -34) | -32 (-36, -29) | -33 (-36, -29) | -23 (-26, -20)
Estimates based on a multiple imputation model that accounts for treatment adherence

Study 5 (RUTHERFORD-2, NCT01763918) was a multicenter, double-blind, randomized, placebo-controlled, 12-week trial in 329 patients with HeFH on statins with or without other lipid-lowering therapies. Patients were randomized to receive subcutaneous injections of REPATHA 140 mg every two weeks, 420 mg once monthly, or placebo. HeFH was diagnosed by the Simon Broome criteria (1991). In Study 5, 38% of patients had clinical atherosclerotic cardiovascular disease. The mean age at baseline was 51 years (range: 19 to 79 years), 15% of the patients were ≥ 65 years old, 42% were women, 90% were White, 5% were Asian, and 1% were Black. The average LDL-C at baseline was 156 mg/dL with 76% of the patients on high-intensity statin therapy.

The differences between REPATHA and placebo in mean percent change in LDL-C from baseline to Week 12 was −61% (95% CI: −67%, −55%; p < 0.0001) and −60% (95% CI: −68%, −52%; p < 0.0001) for the 140 mg every 2 weeks and 420 mg once monthly dosages, respectively. For additional results, see Table 7 and Figure 5.

Table 7. Effect of REPATHA on Lipid Parameters in Patients with HeFH (Mean % Change from Baseline to Week 12 in RUTHERFORD-2)
Treatment Group | LDL-C | Non-HDL-C | Apo B | Total Cholesterol
Placebo every 2 weeks (n = 54) | -1 | -1 | -1 | -2
REPATHA 140 mg every 2 weeks [140 mg every 2 weeks or 420 mg once monthly yield similar reductions in LDL-C] (n = 110) | -62 | -56 | -49 | -42
Mean difference from placebo (95% CI) | -61 (-67, -55) | -54 (-60, -49) | -49 (-54, -43) | -40 (-45, -36)
Placebo once monthly (n = 55) | 4 | 4 | 4 | 2
REPATHA 420 mg once monthly (n = 110) | -56 | -49 | -44 | -37
Mean difference from placebo (95% CI) | -60 (-68, -52) | -53 (-60, -46) | -48 (-55, -41) | -39 (-45, -33)
Estimates based on a multiple imputation model that accounts for treatment adherence

Figure 5. Effect of REPATHA on LDL-C in Patients with HeFH (Mean % Change from Baseline to Week 12 in RUTHERFORD-2)

N = number of patients randomized and dosed in the full analysis set

Estimates based on a multiple imputation model that accounts for treatment adherence

Error bars indicate 95% confidence intervals

Pediatric Patients with HeFH

Study 6 (HAUSER-RCT, NCT02392559) was a randomized, multicenter, placebo-controlled, double-blind, 24-week trial in 157 pediatric patients aged 10 to 17 years with HeFH [see Use in Specific Populations (8.4)]. HeFH was diagnosed by diagnostic criteria for HeFH [Simon Broome Register Group (1991), the Dutch Lipid Clinic Network (1999), MEDPED (1993)] or by genetic testing. Patients were required to be on a low-fat diet and optimized background lipid-lowering therapy. Patients were randomly assigned 2:1 to receive 24 weeks of subcutaneous once monthly 420 mg REPATHA or placebo; 104 patients received REPATHA and 53 patients received placebo. The mean age was 14 years (range: 10 to 17 years), 56% were female, 85% White, 1% Black, 1% Asian, 13% Other, and 8% Hispanic. The mean LDL-C at baseline was 184 mg/dL; 17% of patients were on high-intensity statin, 62% on moderate-intensity statin, and 13% on ezetimibe.

The difference between REPATHA and placebo in mean percent change in LDL-C from baseline to Week 24 was −38% (95% CI: −45%, −31%; p < 0.0001). For additional results, see Table 8 and Figure 6.

Figure 6. Effect of REPATHA on LDL-C in Pediatric Patients with HeFH (Mean % Change from Baseline in HAUSER-RCT)

EvoMab = evolocumab; LDL-C = low density lipoprotein cholesterol; QM = monthly (subcutaneous)

N = number of patients randomized and dosed in the full analysis set.
Vertical lines represent the standard error around the mean. Plot is based on observed data and no imputation is used for missing values.

Table 8. Effect of REPATHA on Lipid Parameters in Pediatric Patients with HeFH (Mean % Change from Baseline to Week 24 in HAUSER-RCT)
Treatment Group | LDL-C | Non-HDL-C | Apo B | Total Cholesterol
Placebo once monthly (n = 53) | -6 | -6 | -2 | -5
REPATHA 420 mg once monthly (n = 104) | -44 | -41 | -35 | -32
Mean difference from placebo (95% CI) | -38 (-45, -31) | -35 (-42, -28) | -32 (-39, -26) | -27 (-32, -21)
All adjusted p-values < 0.0001.
n = number of patients randomized and dosed in the full analysis set.

Adults and Pediatric Patients with HoFH

Study 7 (TESLA, NCT01588496) was a multicenter, double-blind, randomized, placebo-controlled, 12-week trial in 49 patients (not on lipid-apheresis therapy) with HoFH. In this trial, 33 patients received subcutaneous injections of 420 mg of REPATHA once monthly and 16 patients received placebo as an adjunct to other lipid-lowering therapies (e.g., statins, ezetimibe). The mean age at baseline was 31 years, 49% were women, 90% White, 4% were Asian, and 6% other. The trial included 10 adolescents (ages 13 to 17 years), 7 of whom received REPATHA. The mean LDL-C at baseline was 349 mg/dL with all patients on statins (atorvastatin or rosuvastatin) and 92% on ezetimibe. The diagnosis of HoFH was made by genetic confirmation or a clinical diagnosis based on a history of an untreated LDL-C concentration > 500 mg/dL together with either xanthoma before 10 years of age or evidence of HeFH in both parents.

The difference between REPATHA and placebo in mean percent change in LDL-C from baseline to Week 12 was −31% (95% CI: −44%, −18%; p < 0.0001). For additional results, see Table 9.

Patients known to have two LDL-receptor negative alleles (little to no residual function) did not respond to REPATHA.

Table 9. Effect of REPATHA on Lipid Parameters in Patients with HoFH (Mean % Change from Baseline to Week 12 in TESLA)
Treatment Group | LDL-C | Non-HDL-C | Apo B | Total Cholesterol
Placebo once monthly (n = 16) | 9 | 8 | 4 | 8
REPATHA 420 mg once monthly (n = 33) | -22 | -20 | -17 | -17
Mean difference from placebo (95% CI) | -31 (-44, -18) | -28 (-41, -16) | -21 (-33, -9) | -25 (-36, -14)
Estimates based on a multiple imputation model that accounts for treatment adherence

Study 8 (TAUSSIG, NCT01624142) was a multicenter, open-label 5-year extension study with REPATHA in 106 patients with HoFH, who were treated with REPATHA as an adjunct to other lipid-lowering therapies. The study included 14 pediatric patients (ages 13 to 17 years). All patients in the study were initially treated with REPATHA 420 mg once monthly except for those receiving lipid apheresis at enrollment, who began with REPATHA 420 mg every 2 weeks. Dose frequency in non-apheresis patients could be titrated up to 420 mg once every 2 weeks based on LDL-C response and PCSK9 levels.

A total of 48 patients with HoFH received REPATHA 420 mg once monthly for at least 12 weeks in Study 8 followed by REPATHA 420 mg every 2 weeks for at least 12 weeks. Mean percent change from baseline in LDL-C were −20% at Week 12 of 420 mg once monthly treatment and −30% at Week 12 of 420 mg every 2 weeks treatment, based on available data.

Study 9 (HAUSER-OLE, NCT02624869) was an open-label, single-arm, multicenter, 80-week study to evaluate the safety, tolerability, and efficacy of REPATHA for LDL-C reduction in pediatric patients aged 10 to 17 years with HoFH [see Use in Specific Populations (8.4)]. Patients were on a low-fat diet and receiving background lipid-lowering therapy. Overall, 12 patients with HoFH received 420 mg REPATHA subcutaneously once monthly. The mean age was 12 years (range 11 to 17 years), 17% were female, 75% White, 17% Asian, and 8% Other. Median (Q1, Q3) LDL-C at baseline was 398 (343, 475) mg/dL, and all patients were on statins (atorvastatin or rosuvastatin) and ezetimibe. No patients were receiving lipid apheresis. The diagnosis of HoFH was made by genetic confirmation in all patients but enrollment by a clinical diagnosis was permitted. The median (Q1, Q3) percent change in LDL-C from baseline to Week 80 was −14% (−41, 4). Two of the 3 subjects with < 5% LDLR activity responded to evolocumab treatment.

16 HOW SUPPLIED/STORAGE AND HANDLING

REPATHA is a clear to opalescent, colorless to pale yellow solution supplied as follows:

Not Made with Natural Rubber Latex –
140 mg/mL prefilled single-dose SureClick® autoinjector | 2 pack | NDC 72511-393-02
140 mg/mL prefilled single-dose SureClick® autoinjector | 1 pack | NDC 72511-393-01
140 mg/mL prefilled single-dose Syringe | 1 pack | NDC 72511-501-01
420 mg/3.5 mL single-dose Pushtronex® system (on-body infusor with prefilled cartridge) | 1 pack | NDC 72511-770-01

Contains Dry Natural Rubber –
140 mg/mL prefilled single-dose SureClick® autoinjector [The needle cover of the glass prefilled single-dose SureClick® autoinjector and prefilled single-dose syringe contain dry natural rubber (a derivative of latex) that may cause allergic reactions in individuals sensitive to latex [see Warnings and Precautions (5.1)].] | 2 pack | NDC 72511-760-02
140 mg/mL prefilled single-dose Syringe | 1 pack | NDC 72511-750-01

STORAGE AND HANDLING

Store refrigerated at 2°C to 8°C (36°F to 46°F) in the original carton to protect from light. Do not freeze. Do not shake.

For convenience, REPATHA may be kept at room temperature at 68°F to 77°F (20°C to 25°C) in the original carton for 30 days. If not used within the 30 days, discard REPATHA.

17 PATIENT COUNSELING INFORMATION

Advise the patient and/or caregiver to read the FDA-Approved Patient Labeling (Patient Information and Instructions for Use).

Hypersensitivity

Inform patients that serious hypersensitivity reactions (e.g., angioedema) have been reported in patients treated with REPATHA. Advise patients on the symptoms of hypersensitivity reactions and instruct them to discontinue REPATHA and seek medical attention promptly, if such symptoms occur.

Latex-Sensitivity

Instruct patients to inform their healthcare provider if they are sensitive to latex. Inform patients that REPATHA is available as prefilled single-dose SureClick® autoinjectors and prefilled single-dose syringes that either contain dry natural rubber (a derivative of latex) in the needle cover or are not made with natural rubber latex, and the carton and Instructions for Use state if the product contains dry natural rubber. Advise latex-sensitive patients that the needle cover of the glass prefilled single-dose SureClick® autoinjector and prefilled single-dose syringe that contain dry natural rubber (a derivative of latex) may cause allergic reactions in individuals sensitive to latex. [see How Supplied/Storage and Handling (16)].

Pregnancy

Advise women who are exposed to REPATHA during pregnancy that there is a pregnancy safety study that monitors pregnancy outcomes. Encourage these patients to report their pregnancy to Amgen at 1-800-77-AMGEN (1-800-772-6436) or https://wwwext.amgen.com/products/global-patient-safety/adverse-event-reporting [see Use in Specific Populations (8.1)].

Administration

Provide guidance to patients and caregivers on proper subcutaneous administration technique and how to use the prefilled single-dose SureClick® autoinjector, prefilled single-dose syringe, or single-dose on-body infusor with prefilled cartridge correctly. Inform patients that it may take up to 15 seconds to administer REPATHA using the prefilled single-dose SureClick® autoinjector or prefilled single-dose syringe and about 5 minutes to administer REPATHA using the single-dose on-body infusor with prefilled cartridge.

The single-dose on-body infusor with prefilled cartridge is not made with natural rubber latex.

For more information about REPATHA, go to www.REPATHA.com or call 1-844-REPATHA (1-844-737-2842).

REPATHA® (evolocumab)

Manufactured by:
Amgen Inc.
One Amgen Center Drive
Thousand Oaks, California 91320-1799
U.S. License Number 1080
Patent: http://pat.amgen.com/repatha/
© 2015-2021, 2024-2025 Amgen Inc. All rights reserved.
v12

Patient Information
REPATHA® (ri-PAth-a)
(evolocumab)
injection, for subcutaneous use

What is REPATHA?
REPATHA is an injectable prescription medicine used:

- to reduce the risk of major adverse cardiovascular (CV) events, such as death from cardiovascular disease, heart attack, stroke, certain types of chest pain conditions (unstable angina) requiring hospitalization, or certain types of heart surgery, in adults at increased risk for these events.
- Along with diet and exercise to reduce low-density lipoprotein (LDL) or bad cholesterol in:
  - adults with high blood cholesterol levels called hypercholesterolemia.
  - adults and children aged 10 years and older with a type of high cholesterol called heterozygous familial hypercholesterolemia (HeFH).
  - adults and children aged 10 years and older with a type of high cholesterol called homozygous familial hypercholesterolemia (HoFH).

It is not known if REPATHA is safe and effective in children with HeFH or HoFH who are younger than 10 years of age or in children with other types of hypercholesterolemia.

Who should not use REPATHA?
Do not use REPATHA if you or your child are allergic to evolocumab or to any of the ingredients in REPATHA. See the end of this leaflet for a complete list of ingredients in REPATHA.

What should I tell my healthcare provider before using REPATHA?
Before you or your child start using REPATHA, tell your healthcare provider about all your medical conditions, including if you or your child:

- are allergic to rubber or latex. REPATHA is available as prefilled single-dose SureClick® autoinjectors and prefilled single-dose syringes that either contain dry natural rubber (a derivative of latex) in the needle cover or are not made with natural rubber latex. The carton and "Instructions for Use" will state if your prefilled single-dose SureClick autoinjector or prefilled single-dose syringe contains dry natural rubber.
  - The single-dose Pushtronex® system (on-body infusor with prefilled cartridge) is not made with natural rubber latex.
- are pregnant or plan to become pregnant. It is not known if REPATHA will harm your unborn baby. Tell your healthcare provider if you become pregnant while taking REPATHA.
- are breastfeeding or plan to breastfeed. You and your healthcare provider should decide if you will take REPATHA or breastfeed.

If you or your child are pregnant or breastfeed during REPATHA treatment, you are encouraged to call Amgen at 1-800-772-6436 (1-800-77-AMGEN) or visit https://wwwext.amgen.com/products/global-patient-safety/adverse-event-reporting to share information about the health of you and your baby or your child and your child's baby.
Tell your healthcare provider or pharmacist about any prescription and over-the-counter medicines, vitamins, or herbal supplements you or your child take.

How should I use REPATHA?

- See the detailed "Instructions for Use" that comes with this Patient Information about the right way to prepare and give REPATHA.
- Use REPATHA exactly as your healthcare provider tells you or your child to use it.
- REPATHA is given under the skin (subcutaneously), every 2 weeks or 1 time each month.
  - If you or your child have HoFH, the recommended starting dose is 420 mg one time each month. After 12 weeks, your healthcare provider may decide to increase the dose to 420 mg every two weeks. If you or your child receive lipid apheresis, your healthcare provider may decide to start you or your child on a dose of 420 mg every two weeks to match with the apheresis treatment and you or your child should take the dose after the apheresis treatment.
- REPATHA comes as a prefilled single-dose (1 time) autoinjector (SureClick autoinjector), as a prefilled single-dose syringe or as a single-dose Pushtronex system (on-body infusor with prefilled cartridge). Your healthcare provider will prescribe the type and dose that is best for you or your child.
- If your healthcare provider prescribes you or your child the 420 mg dose, you or your child may use:
  - a single-dose on-body infusor with prefilled cartridge to give the injection over 5 minutes, or
  - 3 separate injections in a row, using a different prefilled single-dose SureClick autoinjector or prefilled single-dose syringe for each injection. Give all of these injections within 30 minutes.
- If your healthcare provider decides that you or your child or a caregiver can give REPATHA, you or your child or your caregiver should receive training on the right way to prepare and inject REPATHA. Do not try to inject REPATHA until you or your child have been shown the right way by your healthcare provider or nurse.
  - If you or your child are using the prefilled single-dose SureClick autoinjector, put the yellow safety guard (needle inside) of the prefilled single-dose SureClick autoinjector on the skin before injecting.
- You or your child can inject into the thigh, upper arm, or stomach (abdomen), except for a two-inch area around the belly button.
- Do not choose an area where the skin is tender, bruised, red, or hard. Avoid injecting into areas with scars or stretch marks.
- Always check the label of your prefilled single-dose SureClick autoinjector, prefilled single-dose syringe, or single-dose on-body infusor with prefilled cartridge to make sure you have the correct medicine and the correct dose of REPATHA before each injection.
- If you or your child forget to use REPATHA or are not able to take the dose at the regular time, inject your or your child's missed dose as soon as you remember, as long as it is within 7 days of the missed dose.
  - If it is more than 7 days from the missed dose and you or your child are using the every-2-week dose, inject the next dose based on the original schedule. This will put you or your child back on the original schedule.
  - If it is more than 7 days from the missed dose and you or your child are using the 1 time each-month dose, inject the dose and start a new schedule using this date.

If you or your child are not sure when to take REPATHA after a missed dose, ask your healthcare provider or pharmacist.

- If your healthcare provider has prescribed REPATHA along with other cholesterol-lowering medicines for you or your child, follow instructions from your healthcare provider. Read the Patient Information for those medicines.
- If you or your child use more REPATHA than you should, talk to your healthcare provider or pharmacist.
- Do not stop using REPATHA without talking with your healthcare provider. If you or your child stop using REPATHA, the cholesterol levels can increase.

What are the possible side effects of REPATHA?
REPATHA can cause serious side effects including:

- Serious Allergic Reactions. Some people taking REPATHA have had serious allergic reactions. Stop taking REPATHA and call your healthcare provider or seek emergency medical help right away if you or your child have any of these symptoms:
  - trouble breathing or swallowing
  - raised bumps (hives)
  - rash, or itching
  - swelling of the face, lips, tongue, throat or arms

The most common side effects of REPATHA include: runny nose, sore throat, symptoms of the common cold, flu or flu-like symptoms, back pain, high blood sugar levels (diabetes) and redness, pain, or bruising at the injection site.
Tell your healthcare provider if you or your child have any side effect that bothers you or that does not go away.
These are not all the possible side effects of REPATHA. Ask your healthcare provider or pharmacist for more information.
Call your healthcare provider for medical advice about side effects. You may report side effects to FDA at 1-800-FDA-1088.

How should I store REPATHA?

- Store REPATHA in the refrigerator between 36°F to 46°F (2°C to 8°C). Store REPATHA in the original carton until use to protect it from light.
- If needed, REPATHA can be stored at room temperature between 68°F to 77°F (20°C to 25°C) in the original carton for up to 30 days. Throw away REPATHA that has been stored at room temperature for more than 30 days.
- Do not freeze REPATHA.
- Do not shake REPATHA.

Keep REPATHA and all medicines out of the reach of children.

General information about the safe and effective use of REPATHA.
Medicines are sometimes prescribed for purposes other than those listed in a Patient Information leaflet. Do not use REPATHA for a condition for which it was not prescribed. Do not give REPATHA to other people, even if they have the same symptoms that you or your child have. It may harm them.
You can ask your pharmacist or healthcare provider for information about REPATHA that is written for healthcare professionals.

What are the ingredients in REPATHA?

- Active Ingredient: evolocumab
- Inactive Ingredients: proline; acetate; polysorbate 80; water for injection, USP; and sodium hydroxide.

Manufactured by: Amgen Inc. One Amgen Center Drive, Thousand Oaks, California 91320-1799.
U.S. License Number 1080
Patent: http://pat.amgen.com/repatha/
© 2017-2021, 2024-2025 Amgen Inc. All rights reserved.
For more information about REPATHA, go to www.REPATHA.com or call 1-844-REPATHA (1-844-737-2842).

This Patient Information has been approved by the U.S. Food and Drug Administration.
v10

Revised: 08/2025

Instructions for Use:
Pushtronex® System for
Repatha® (ri-PAth-a)
(evolocumab)
Single-Dose On-Body Infusor and Prefilled Cartridge

Guide to parts

Prefilled Cartridge

On-Body Infusor

Front view

Back view

Important: Needle is inside.

Important

Before you use the on-body infusor and prefilled cartridge for use with Repatha (evolocumab), read this important information:

- It is important that you do not try to give yourself the injection unless you have received training from your healthcare provider.
- Children who are 10 to 17 years of age should use the on-body infusor and prefilled cartridge under adult supervision, as instructed by the healthcare provider.

Storing your on-body infusor and prefilled cartridge

- Keep the on-body infusor and prefilled cartridge in the original carton to protect from light or physical damage.
- The on-body infusor and prefilled cartridge must be kept in the refrigerator 36°F to 46°F (2°C to 8°C).
- For your injection, take your on-body infusor and prefilled cartridge out of the refrigerator and let them sit at room temperature for at least 45 minutes before you inject.
- After you remove the on-body infusor and prefilled cartridge from the refrigerator, they should be kept at room temperature at 68°F to 77°F (20°C to 25°C) in the original carton and must be used within 30 days.
- Do not store the on-body infusor and prefilled cartridge in temperatures above 77°F (25°C) such as in your vehicle's glove box or trunk. Do not freeze.

Using your on-body infusor and prefilled cartridge

- Do not shake the on-body infusor or prefilled cartridge.
- Do not remove the on-body infusor and prefilled cartridge from the box or clear tray until you are ready to inject.
- Do not touch the start button until you place the loaded on-body infusor and prefilled cartridge onto your skin and are ready to inject.
- After you insert the cartridge into the on-body infusor, make sure you give your injection within 5 minutes. Waiting longer than 5 minutes can dry out the medicine.
- You can only press the start button 1 time. If an error occurs, the on-body infusor cannot be used.
- Do not use the on-body infusor and prefilled cartridge if either has been dropped onto a hard surface. Part of the on-body infusor and prefilled cartridge may be broken even if you cannot see the break. Use a new on-body infusor and prefilled cartridge.
- Do not reuse the on-body infusor and prefilled cartridge. The on-body infusor and prefilled cartridge are for single-dose only.
- Do not let the on-body infusor get wet from water or any other liquids. It contains electronics that should not get wet.
- The single-dose on-body infusor for subcutaneous injection is made to only be used with the prefilled cartridge.
- Moderate physical activities can be done during the injection process, such as walking, reaching and bending.
- Do not use the on-body infusor and prefilled cartridge after the expiration date on the carton.
- The on-body infusor and prefilled cartridge are not made with natural rubber latex.

A healthcare provider who knows how to use the on-body infusor should be able to answer your questions. For more information, call 1-844-REPATHA (1-844-737-2842) or visit www.REPATHA.com.
Keep the on-body infusor and prefilled cartridge out of the reach of children.

Step 1: Prepare

1A

Remove the on-body infusor and prefilled cartridge carton from the refrigerator. Wait at least 45 minutes before injecting for the on-body infusor and prefilled cartridge in the carton to naturally reach room temperature.

- Do not try to warm the prefilled cartridge by using a heat source such as hot water or a microwave.

In any above cases, use a new on-body infusor and prefilled cartridge and call 1-844-REPATHA (1-844-737-2842) or visit www.REPATHA.com.

1B

Open the carton and peel away the white paper cover. Remove the plastic cover from the clear tray.

Leave the on-body infusor and prefilled cartridge in the clear tray until you are ready to inject.

- Do not touch the start button until the on-body infusor is on the skin and you are ready to inject.
- Do not use if the white paper cover is missing or damaged.

1C

Gather all materials needed for your injection and then wash your hands well with soap and water.

On a clean, well-lit work surface, place the:

- Clear tray containing the on-body infusor and prefilled cartridge
- Alcohol wipes
- Cotton ball or gauze pad
- Adhesive bandage
- Sharps disposal container

1D

To securely attach the on-body infusor, prepare and clean an injection site that is less likely to have body hair, or you can trim the area. Use a firm and flat skin surface.

You can use:

- Your thigh
- Stomach area (abdomen), except for a two-inch area right around your navel
- Outer area of upper arm (only if someone else is giving the injection)

Clean your injection site with an alcohol wipe. Let your skin dry.

- Do not touch this area again before injecting.
- Do not inject into areas where the skin is tender, bruised, red or hard. Avoid injecting into areas with wrinkles, skin folds, scars, stretch marks, moles and excessive hair.

Important: To attach the on-body infusor securely, it is important to use a firm and flat skin surface.

Step 2: Get ready

2A

Open the on-body infusor by swinging the cartridge door to the right. Then, leave the door open. Do not close the cartridge door before the cartridge is loaded.

If you accidently close the cartridge door, press on the left side of the door to release the door latch.
If you are still unable to open the door, call 1-844-REPATHA (1-844-737-2842) or visit www.REPATHA.com.
Do not press the start button until you are ready to inject.

2B

Inspect the cartridge.

Check the expiration date: do not use if this date has passed.
Make sure the medicine in the cartridge is clear and colorless to slightly yellow.

- Do not use if the medicine is cloudy or discolored or contains flakes or particles.
- Do not use if any part of the cartridge looks cracked or broken.
- Do not use if pieces of the cartridge are missing or not securely attached.

In any above cases, use a new on-body infusor and prefilled cartridge and call 1-844-REPATHA (1-844-737-2842) or visit www.REPATHA.com.

2C

Clean the cartridge bottom.

Grab Here

With 1 hand, hold the cartridge barrel and clean the cartridge bottom with an alcohol wipe.

- Do not remove or rotate the cartridge top or bottom.
- Do not touch the bottom of the cartridge after cleaning with alcohol wipe.

2D

Load the cleaned cartridge into the on-body infusor and firmly press on the top until it is secured in place. Make sure that you give your injection within 5 minutes after loading the cartridge. Do not insert the cartridge more than 5 minutes before injection. This can dry out the medicine.

Insert the cartridge bottom first.

- Do not touch the start button until you have placed the loaded on-body infusor on your skin.

2E

Swing the door to the left. Then, squeeze firmly until it snaps shut. Apply enough pressure when closing the door and make sure there is a "snap" before going to the next step.

Make sure the cartridge fits securely in the on-body infusor before you close the door.

- Do not close the door if the cartridge is missing or not fully inserted.
- Do not touch the start button until you have placed the loaded on-body infusor on your skin.

Important: After you load the on-body infusor, go to the next step right away.

Step 3: Inject

3A

Peel away both green pull tabs to show the adhesive. The on-body infusor is on when the blue status light flashes.

You must remove both green pull tabs to turn the loaded on-body infusor on. You will hear beeping and see a flashing blue status light.

- Do not pull the skin adhesive backing off the on-body infusor.
- Do not touch the skin adhesive.
- Do not touch the start button until you have placed the loaded on-body infusor on your skin.
- Do not touch the needle cover area.
- Do not place the loaded on-body infusor on your body if the red status light flashes continuously.
- Do not fold the skin adhesive over onto itself.

3B

Choose your on-body infusor injection site. Only use the outer arm if someone else is giving the injection.

Stomach area placement

Thigh placement

or

Stretch method for stomach

Do not stretch for thigh

Important: Adjust your body posture to avoid skin folds and bulges.

3C

When the blue light flashes, the on-body infusor is ready. Keep the stretch (stomach area method only). Hold the loaded on-body infusor with the blue light visible, and place it on your skin. You may hear beeps.

Stomach area placement

Thigh placement

or

The loaded on-body infusor will lay flat on your body. Make sure all of the adhesive is attached to your skin. Run a finger around the adhesive edges to secure it.

Make sure clothing does not get in the way of the loaded on-body infusor, and you can see the blue light at all times.

- Do not move the loaded on-body infusor after it has been placed onto your skin.

3D

Firmly press and release the start button. A flashing green light and a click signals the injection has started.

- You may hear a pumping sound.
- You may feel a pinch.
- Make sure you see a green, flashing status light.
- You may hear beeps that mean your injection has started.

Important: If medication leaks from the on-body infusor, call 1-844-REPATHA (1-844-737-2842) or visit www.REPATHA.com.

3E

The injection takes about 5 minutes to finish. The status light turns solid green, and the device beeps, when done.

It is okay to hear a pumping sound start and stop during injection.

Injection is finished when:

- The status light changes to solid green.
- You hear several beeps.
- The plunger fills medicine window all the way.

Step 4: Finish

4A

When the injection is done, grab the skin adhesive to carefully peel the on-body infusor off skin. After removal, check the medicine window. The green light should now be off.

Used plunger filling medicine window

Check to see that the used plunger fills the medicine window all the way, and the green solid light turns off, letting you know all medicine has been injected. If the plunger did not fill the window, call 1-844-REPATHA (1-844-737-2842) or visit www.REPATHA.com.

- The used on-body infusor will beep when removed from your skin.
- It is normal to see a few drops of fluid on your skin after you remove the used on-body infusor.

4B

Throw away the used on-body infusor in a sharps container.

- The on-body infusor contains batteries, electronics, and a needle.
- Put the used on-body infusor in a FDA-cleared sharps disposal container right away after use. Do not throw away (dispose of) the on-body infusor in your household trash.
- If you do not have a FDA-cleared sharps disposal container, you may use a household container that is:
  - made of a heavy-duty plastic,
  - can be closed with a tight-fitting, puncture-resistant lid, without sharps being able to come out,
  - upright and stable during use,
  - leak-resistant, and
  - properly labeled to warn of hazardous waste inside the container.
- When your sharps disposal container is almost full, you will need to follow your community guidelines for the right way to dispose of your sharps disposal container. There may be state or local laws about how you should throw away used needles and syringes. For more information about safe sharps disposal, and for specific information about sharps disposal in the state that you live in, go to the FDA's website at: http://www.fda.gov/safesharpsdisposal.
- Do not dispose of your used sharps disposal container in your household trash unless your community guidelines permit this. Do not recycle your used sharps disposal container.
- Do not recycle the on-body infusor or sharps disposal container or throw them into household trash.

Important: Always keep the sharps disposal container out of the reach of children.

4C

Check the injection site.

If there is blood, press a cotton ball or gauze pad on your injection site. Do not rub the injection site. Apply an adhesive bandage if needed.

Troubleshooting

What do I do if the loaded on-body infusor status light continuously flashes red and I hear beeps?

Stop using the loaded on-body infusor. If the on-body infusor is attached to your body, carefully remove it. Call 1-844-REPATHA (1-844-737-2842) or visit www.REPATHA.com.

Commonly Asked Questions

What if I hear the on-body infusor beep and see a red blinking light when it is on my body?

This means that an error has happened. When this happens, the injection will stop by itself. Remove the on-body infusor from your body by slowly and carefully peeling it off of your skin, call 1-844-REPATHA (1-844-737-2842) or visit www.REPATHA.com.

What should I do if the on-body infusor comes off my body during the injection?

Though unlikely, if the on-body infusor comes off during the injection, the on-body infusor will make a beeping sound, you will see the blinking red light, and the on-body infusor will stop. The loaded on-body infusor can no longer be used, and do not reapply to your body. Call 1-844-REPATHA (1-844-737-2842) or visit www.REPATHA.com.

What if I push the start button before I place the on-body infusor on my skin?

If you have removed the adhesive backing and pressed the start button, the on-body infusor will make a beeping sound and you will see the blinking red light. The on-body infusor will stop. Stop using the on-body infusor, call 1-844-REPATHA (1-844-737-2842) or visit www.REPATHA.com.

What if the on-body infusor does not beep and the blue status light does not blink when I remove the pull tabs?

Check to see if both green pull tabs have been fully removed from the on-body infusor, including the adhesive paper over the battery strip and needle cover. If both green pull tabs have been fully removed and the on-body infusor still does not turn on, use a new on-body infusor and prefilled cartridge. Call 1-844-REPATHA (1-844-737-2842) or visit www.REPATHA.com.

What if I push the start button and nothing happens?

Remove the on-body infusor by slowly and carefully peeling it away from your skin. Do not reapply the same on-body infusor that you have already placed on your skin. Call 1-844-REPATHA (1-844-737-2842) or visit www.REPATHA.com.

What if I cannot open the cartridge door to insert the cartridge?

To open the on-body infusor door, press on the left side of the door to release the door latch. If you are still unable to open the door, call 1-844-REPATHA (1-844-737-2842) or visit www.REPATHA.com.

This Instructions for Use has been approved by the U.S. Food and Drug Administration.

Manufactured by:
Amgen Inc.
One Amgen Center Drive
Thousand Oaks, CA 91320-1799
© 2015-2021 Amgen Inc.
All rights reserved.
<part number> Revised: 9/2021 v8

U.S. License Number 1080

Additional environmental conditions
Relative humidity range is 15% to 85%.
Altitude range is -984 feet to 11483 feet (-300 meters to 3500 meters).
During injection, keep the on-body infusor a minimum of 12 inches (30 cm) away from other electronics such as cellular phones.
Warning: Do not modify the device.
Warning: Do not expose the on-body infusor for Repatha to Magnetic Resonance (MR) Environment (e.g., MRI).
On-body infusor operating temperature range is 59°F to 104°F (15°C to 40°C).
On-body infusor complies with IEC 60601-1 3.1 edition and IEC 60601-1-2: 2014.
www.devicepatents.com.

SYMBOL TABLE

Do not re-use

Serial number

Type BF Applied Part

Do not use if packaging is damaged

On-Body Infusor containing 420 mg/3.5 mL (120 mg/mL)

Sterilized using ethylene oxide

Refer to Instructions for Use

Lot number

Keep dry

Open here

MR Unsafe

INSTRUCTIONS FOR USE REPATHA® [ri-PAth-a] (evolocumab) injection, for subcutaneous use 140 mg/mL prefilled single-dose SureClick® autoinjector (contains dry natural rubber)

This Instructions for Use contains information on how to inject REPATHA with a SureClick autoinjector.

If your healthcare provider decides that you or a caregiver may be able to give your injections of REPATHA at home, you should receive training on the right way to prepare and inject REPATHA. Do not try to inject yourself until you have been shown the right way to give the injections by your healthcare provider or nurse.

The medicine in the REPATHA autoinjector is for injection under the skin (subcutaneous injection). See the REPATHA Patient Information for information about REPATHA.

Getting to know the prefilled autoinjector

Important Information You Need to Know Before Injecting REPATHA

- It is important that you do not try to give the injection until you have fully read and understood this Instructions for Use.
- The orange cap on the REPATHA SureClick autoinjector contains a yellow safety guard (located inside the cap) that contains dry natural rubber, which is made from latex. Tell your healthcare provider if you are allergic to latex.
- Check the autoinjector label and prescription to make sure you have the correct medicine and dose.
- Do not use the autoinjector if the carton is damaged or the seal is broken.
- Do not use the autoinjector after the expiration date on the label.
- Do not shake the autoinjector.
- Do not remove the orange cap from the autoinjector until you are ready to inject.
- Do not use the autoinjector if it has been frozen.
- Do not use the autoinjector if it has been dropped on a hard surface. Part of the autoinjector may be broken even if you cannot see the break. Use a new autoinjector, and call 1-844-REPATHA (1-844-737-2842).

Frequently asked questions:
For additional information and answers to frequently asked questions, visit www.repatha.com.

Where to get help:
If you want more information or help using REPATHA:

- Contact your healthcare provider,
- Visit www.repatha.com, or
- Call 1-844-REPATHA (1-844-737-2842).

Storing and Preparing to Inject REPATHA

1 | Refrigerate the autoinjector carton until you are ready to use it.; - Keep the autoinjector in the refrigerator between 36°F to 46°F (2°C to 8°C). - Keep the autoinjector in the original carton to protect it from light or physical damage. - Do not freeze the autoinjector. - Do not store the autoinjector in extreme heat or cold. For example, avoid storing in your vehicle's glove box or trunk.
Important: Keep the autoinjector and all medicines out of the sight and reach of children.
WAIT
2 | Wait 30 minutes for the autoinjector to reach room temperature.; - Remove the number of autoinjectors you need for your injection and put any unused autoinjectors back into the refrigerator. - Let the autoinjector warm up naturally. - Do not heat the autoinjector with hot water, a microwave, or direct sunlight. - Do not shake the autoinjector at any time. - Using the autoinjector at room temperature makes sure the full dose is delivered and allows for a more comfortable injection.
3 | You may keep REPATHA at room temperature for up to 30 days, if needed.; - For example, when you are traveling, you may keep REPATHA at room temperature. - Keep it at room temperature between 68°F to 77°F (20°C to 25°C). - Record the date you removed it from the refrigerator and use it within 30 days.
Important: Place the autoinjector in a sharps disposal container if it has reached room temperature and has not been used within 30 days.
4 | Inspect the medicine. It should be clear and colorless to slightly yellow.; - It is okay to see air bubbles. - Do not use the autoinjector if the medicine is cloudy, discolored, or contains flakes or particles.
Important: If the medicine is cloudy, discolored, or contains flakes or particles, or if the autoinjector is damaged or expired, call 1-844-REPATHA (1-844-737-2842).
5 | Check the expiration date (Exp.) and inspect the autoinjector for damage.; - Do not use the autoinjector if the expiration date has passed. - Do not use the autoinjector if: - the orange cap is missing or loose in carton, - it has cracks or broken parts, or - it has been dropped on a hard surface.

Getting Ready to Inject REPATHA

6

Gather and place the following items for your injection on a clean, flat, and well-lit surface:

- REPATHA autoinjector (room temperature),
- Sharps disposal container [see Completing the Injection and Disposal],
- Alcohol wipe,
- Adhesive bandage, and
- Cotton balls or gauze pads.

7

Select 1 of these injection sites.

- Select the thigh or stomach (except for 2 inches around the belly button).
- Someone else can inject in your thigh, stomach, or back of your upper arm.
- Change injection site each time, shifting the area of the injection to avoid skin irritation.

Important: Avoid areas with scars or stretch marks, or where the skin is tender, bruised, red, hard, raised, thick or scaly skin patch, or lesion.

8

Wash your hands thoroughly with soap and water.

9

Clean the injection site with an alcohol wipe.

- Let the skin dry on its own.
- Do not touch this area again before injecting.

Injecting REPATHA

Important: Only remove the orange cap when you can inject right away (within 5 minutes) because the medicine can dry out. Do not recap.

10

Grasp the autoinjector so you can see the window. Pull the orange cap straight off. You may need to pull hard.

- Do not twist, bend, or wiggle the orange cap to pull it off.
- Never put the orange cap back on. It may damage the needle.
- Do not put your finger inside the yellow safety guard.
- It is normal to see a drop of medicine come out of the needle or yellow safety guard.

11

Stretch or pinch the skin to create a firm surface at the injection site until the injection is finished. Place the yellow safety guard straight against the skin.

- Make sure you can see the window.
- Make sure the autoinjector is positioned straight on the injection site (at a 90-degree angle).

PUSH
and hold against skin

12

Firmly push the autoinjector down until the yellow safety guard stops moving. Hold the autoinjector down, do not lift.

- The yellow safety guard pushes in and unlocks the gray start button.

PRESS
gray start button

13

Keep pushing the autoinjector down and press the gray start button to start the injection.

- You may hear or feel a click.
- The window starts to turn yellow.
- It is okay to let go of the gray start button.

WATCH
window will turn fully yellow

14

Keep pushing the autoinjector down. Wait for the window to turn fully yellow.

- The injection may take up to 15 seconds to complete.
- You may hear or feel a click.
- After the window turns fully yellow, lift the autoinjector away from the skin.
- The yellow safety guard locks around the needle.

Completing the Injection and Disposal

CONFIRM

15

Confirm a full dose of medicine was injected.

- Do not touch the yellow safety guard.
- A small drop of liquid on the injection site is okay.

Important: If the window has not turned fully yellow, or if it looks like the medicine is still coming out, a full dose was not injected. Call your healthcare provider right away.

16

Check the injection site.

- Do not rub the injection site.
- If there is blood, press a cotton ball or gauze pad on your injection site.
- Apply an adhesive bandage if necessary.

17

Place the used autoinjector and orange cap in an FDA-cleared sharps disposal container.

Important: Do not throw away the autoinjector in your household trash.

- Do not reuse the autoinjector.
- Do not touch the yellow safety guard.

Additional information about your sharps disposal container
If you do not have an FDA-cleared sharps disposal container, you may use a household container that is:

- made of a heavy-duty plastic,
- can be closed with a tight-fitting, puncture-resistant lid, without sharps being able to come out,
- upright and stable during use,
- leak-resistant, and
- properly labeled to warn of hazardous waste inside the container.

Disposing of sharps disposal containers:
When your sharps disposal container is almost full, you will need to follow your community guidelines for the right way to dispose of your sharps disposal container.

There may be state or local laws about how you should throw away used needles and syringes.

For more information about safe sharps disposal, and for specific information about sharps disposal in the state that you
live in, go to the FDA's website at:
http://www.fda.gov/safesharpsdisposal

Do not dispose of your used sharps disposal container in your household trash unless your community guidelines permit this.

Do not recycle your used sharps disposal container.

Keep the autoinjector and sharps disposal container out of the sight and reach of children.

For more information or help call 1-844-REPATHA (1-844-737-2842).

REPATHA (evolocumab)

Manufactured by:
Amgen Inc.
One Amgen Center Drive
Thousand Oaks, California 91320-1799
U.S. License Number 1080

© 2015-2022, 2024-2025 Amgen Inc.
All rights reserved.
1XXXXXX
This Instructions for Use has been approved by the U.S. Food and Drug Administration.
Revised: 08/2025
v12

INSTRUCTIONS FOR USE REPATHA® [ri-PAth-a] (evolocumab) injection, for subcutaneous use 140 mg/mL prefilled single-dose SureClick® autoinjector

This Instructions for Use contains information on how to inject REPATHA with a SureClick autoinjector.

If your healthcare provider decides that you or a caregiver may be able to give your injections of REPATHA at home, you should receive training on the right way to prepare and inject REPATHA. Do not try to inject yourself until you have been shown the right way to give the injections by your healthcare provider or nurse.

The medicine in the REPATHA autoinjector is for injection under the skin (subcutaneous injection). See the REPATHA Patient Information for information about REPATHA.

Getting to know the prefilled autoinjector

Important Information You Need to Know Before Injecting REPATHA

- It is important that you do not try to give the injection until you have fully read and understood this Instructions for Use.
- Check the autoinjector label and prescription to make sure you have the correct medicine and dose.
- Do not use the autoinjector if the carton is damaged or the seal is broken.
- Do not use the autoinjector after the expiration date on the label.
- Do not shake the autoinjector.
- Do not remove the orange cap from the autoinjector until you are ready to inject.
- Do not use the autoinjector if it has been frozen.
- Do not use the autoinjector if it has been dropped on a hard surface. Part of the autoinjector may be broken even if you cannot see the break. Use a new autoinjector, and call 1-844-REPATHA (1-844-737-2842).
- The autoinjector is not made with natural rubber latex.

Frequently asked questions:
For additional information and answers to frequently asked questions, visit www.repatha.com.

Where to get help:
If you want more information or help using REPATHA:

- Contact your healthcare provider,
- Visit www.repatha.com, or
- Call 1-844-REPATHA (1-844-737-2842).

Storing and Preparing to Inject REPATHA

1 | Refrigerate the autoinjector carton until you are ready to use it.; - Keep the autoinjector in the refrigerator between 36°F to 46°F (2°C to 8°C). - Keep the autoinjector in the original carton to protect it from light or physical damage. - Do not freeze the autoinjector. - Do not store the autoinjector in extreme heat or cold. For example, avoid storing in your vehicle's glove box or trunk.
Important: Keep the autoinjector and all medicines out of the sight and reach of children.
WAIT
2 | Wait 30 minutes for the autoinjector to reach room temperature.; - Remove the number of autoinjectors you need for your injection and put any unused autoinjectors back into the refrigerator. - Let the autoinjector warm up naturally. - Do not heat the autoinjector with hot water, a microwave, or direct sunlight. - Do not shake the autoinjector at any time. - Using the autoinjector at room temperature makes sure the full dose is delivered and allows for a more comfortable injection.
3 | You may keep REPATHA at room temperature for up to 30 days, if needed.; - For example, when you are traveling, you may keep REPATHA at room temperature. - Keep it at room temperature between 68°F to 77°F (20°C to 25°C). - Record the date you removed it from the refrigerator and use it within 30 days.
Important: Place the autoinjector in a sharps disposal container if it has reached room temperature and has not been used within 30 days.
4 | Inspect the medicine. It should be clear and colorless to slightly yellow.; - It is okay to see air bubbles. - Do not use the autoinjector if the medicine is cloudy, discolored, or contains flakes or particles.
Important: If the medicine is cloudy, discolored, or contains flakes or particles, or if the autoinjector is damaged or expired, call 1-844-REPATHA (1-844-737-2842).
5 | Check the expiration date (Exp.) and inspect the autoinjector for damage.; - Do not use the autoinjector if the expiration date has passed. - Do not use the autoinjector if: - the orange cap is missing or loose in carton, - it has cracks or broken parts, or - it has been dropped on a hard surface.

Getting Ready to Inject REPATHA

6

Gather and place the following items for your injection on a clean, flat, and well-lit surface:

- REPATHA autoinjector (room temperature),
- Sharps disposal container [see Completing the Injection and Disposal],
- Alcohol wipe,
- Adhesive bandage, and
- Cotton balls or gauze pads.

7

Select 1 of these injection sites.

- Select the thigh or stomach (except for 2 inches around the belly button).
- Someone else can inject in your thigh, stomach, or back of your upper arm.
- Change injection site each time, shifting the area of the injection to avoid skin irritation.

Important: Avoid areas with scars or stretch marks, or where the skin is tender, bruised, red, hard, raised, thick or scaly skin patch, or lesion.

8

Wash your hands thoroughly with soap and water.

9

Clean the injection site with an alcohol wipe.

- Let the skin dry on its own.
- Do not touch this area again before injecting.

Injecting REPATHA

Important: Only remove the orange cap when you can inject right away (within 5 minutes) because the medicine can dry out. Do not recap.

10

Grasp the autoinjector so you can see the window. Pull the orange cap straight off. You may need to pull hard.

- Do not twist, bend, or wiggle the orange cap to pull it off.
- Never put the orange cap back on. It may damage the needle.
- Do not put your finger inside the yellow safety guard.
- It is normal to see a drop of medicine come out of the needle or yellow safety guard.

11

Stretch or pinch the skin to create a firm surface at the injection site until the injection is finished. Place the yellow safety guard straight against the skin.

- Make sure you can see the window.
- Make sure the autoinjector is positioned straight on the injection site (at a 90-degree angle).

PUSH
and hold against skin

12

Firmly push the autoinjector down until the yellow safety guard stops moving. Hold the autoinjector down, do not lift.

- The yellow safety guard pushes in and unlocks the gray start button.

PRESS
gray start button

13

Keep pushing the autoinjector down and press the gray start button to start the injection.

- You may hear or feel a click.
- The window starts to turn yellow.
- It is okay to let go of the gray start button.

WATCH
window will turn fully yellow

14

Keep pushing the autoinjector down. Wait for the window to turn fully yellow.

- The injection may take up to 15 seconds to complete.
- You may hear or feel a click.
- After the window turns fully yellow, lift the autoinjector away from the skin.
- The yellow safety guard locks around the needle.

Completing the Injection and Disposal

CONFIRM

15

Confirm a full dose of medicine was injected.

- Do not touch the yellow safety guard.
- A small drop of liquid on the injection site is okay.

Important: If the window has not turned fully yellow, or if it looks like the medicine is still coming out, a full dose was not injected. Call your healthcare provider right away.

16 | Check the injection site.; - Do not rub the injection site. - If there is blood, press a cotton ball or gauze pad on your injection site. - Apply an adhesive bandage if necessary.
17 | Place the used autoinjector and orange cap in an FDA-cleared sharps disposal container.
Important: Do not throw away the autoinjector in your household trash.
- Do not reuse the autoinjector.
- Do not touch the yellow safety guard.

Additional information about your sharps disposal container
If you do not have an FDA-cleared sharps disposal container, you may use a household container that is:

- made of a heavy-duty plastic,
- can be closed with a tight-fitting, puncture-resistant lid, without sharps being able to come out,
- upright and stable during use,
- leak-resistant, and
- properly labeled to warn of hazardous waste inside the container.

Disposing of sharps disposal containers:
When your sharps disposal container is almost full, you will need to follow your community guidelines for the right way to dispose of your sharps disposal container.

There may be state or local laws about how you should throw away used needles and syringes.

For more information about safe sharps disposal, and for specific information about sharps disposal in the state that you
live in, go to the FDA's website at:
http://www.fda.gov/safesharpsdisposal

Do not dispose of your used sharps disposal container in your household trash unless your community guidelines permit this.

Do not recycle your used sharps disposal container.

Keep the autoinjector and sharps disposal container out of the sight and reach of children.

For more information or help call 1-844-REPATHA (1-844-737-2842).

REPATHA (evolocumab)

Manufactured by:
Amgen Inc.
One Amgen Center Drive
Thousand Oaks, California 91320-1799
U.S. License Number 1080

© 2024-2025 Amgen Inc.
All rights reserved.
1XXXXXX
This Instructions for Use has been approved by the U.S. Food and Drug Administration.
Revised: 08/2025
v2

Side 1 | Reference Guide REPATHA® [ri-PAth-a] (evolocumab) injection, for subcutaneous use 140 mg/mL | Read Instructions for Use in carton before injecting. Questions? Call 1-844-REPATHA (1-844-737-2842)

1. | Guide to parts | 2. | Wait 30 minutes for the autoinjector to reach room temperature before giving your injection. | 3. | Prepare and clean your injection site. | 4. | Pull the orange cap straight off when you are ready to inject within 5 minutes — the medicine can dry out.
 |  |  | WAIT
 |  |  |  |  |  | Turn over to continue

Side 2 | Reference Guide REPATHA® [ri-PAth-a] (evolocumab) injection, for subcutaneous use 140 mg/mL | Manufactured by: Amgen Inc. Thousand Oaks, CA 91320 © 2019-2022, 2025 Amgen Inc. All rights reserved. 1XXXXXX Revised: 08/2025 v5 | Read other side first; This printed material is recyclable.

5. | Stretch or pinch the skin to create a firm surface at the injection site until the injection is finished. | 6. | PUSH and HOLD down against the skin. Do not lift. | 7. | PRESS gray start button. | 8. | Keep pushing down for up to 15 seconds. Wait for the window to turn fully yellow, then your injection is done.

Instructions for Use
Repatha® (ri-PAth-a)
(evolocumab)
prefilled single-dose syringe
(contains dry natural rubber)

Getting to know the prefilled syringe

Before use

After use

Needle is inside

Important

Before you use a prefilled single-dose syringe, read this important information:

- It is important that you do not try to give the injection until you have fully read and understood this Instructions for Use.
- Check the carton, prefilled syringe label, and prescription to make sure you have the correct medicine and dose.
- Check the expiration date on the REPATHA prefilled syringe carton: do not use if this date has passed.
- It is important that you do not try to give yourself or someone else the injection unless you have received training from your healthcare provider.
- The gray needle cap on the prefilled syringe contains dry natural rubber, which is made from latex. Tell your healthcare provider if you are allergic to latex.

Storage of REPATHA:

- Keep the prefilled syringe in the original carton to protect from light during storage.
- Keep the prefilled syringe in the refrigerator between 36°F to 46°F (2°C to 8°C).
- If removed from the refrigerator, the prefilled syringe should be kept at room temperature at 68°F to 77°F (20°C to 25°C) in the original carton and must be used within 30 days. Place the prefilled syringe in a sharps disposal container if it has reached room temperature and has not been used within 30 days.
- Do not freeze the prefilled syringe or use a prefilled syringe that has been frozen.
- Do not store the prefilled syringe in extreme heat or cold. For example, avoid storing in your vehicle's glove box or trunk.

Do not:

- Do not use the prefilled syringe if the packaging is open or damaged.
- Do not remove the gray needle cap from the prefilled syringe until you are ready to inject.
- Do not use the prefilled syringe if it has been dropped onto a hard surface. Part of the prefilled syringe may be broken even if you cannot see the break. Use a new prefilled syringe and call 1-844-REPATHA (1-844-737-2842).
- Do not use the prefilled syringe after the expiration date.

A healthcare provider who knows how to use the prefilled syringe should be able to answer your questions. For more information, call 1-844-REPATHA (1-844-737-2842) or visit www.REPATHA.com.
Keep the prefilled syringe and all medicines out of the sight and reach of children.

Step 1: Prepare

1 A

Remove the prefilled syringe carton from the refrigerator and wait 30 minutes.

Wait at least 30 minutes for the prefilled syringe in the carton to reach room temperature before injecting.

Using the prefilled syringe at room temperature makes sure the full dose is delivered and allows for a more comfortable injection. Do not heat the syringe. Let it warm up on its own naturally.

Do not try to warm the prefilled syringe by using a heat source such as hot water or microwave.

Do not leave the prefilled syringe in direct sunlight.

Do not shake the prefilled syringe.

1 B

Gather all materials needed for your injection.

Wash your hands thoroughly with soap and water.

On a clean, well-lit, flat work surface, place:

- 1 REPATHA prefilled syringe in carton
- Alcohol wipes
- Cotton ball or gauze pad
- Adhesive bandage
- Sharps disposal container (see Step 4: Finish)

1 C

Choose your injection site.

You can use the:

- front of your thigh
- stomach (abdomen), except for a 2 inch area around your belly button

If someone else is giving you the injection, they can also use the outer area of the upper arm.
Do not choose an area where the skin is tender, bruised, red, or hard. Avoid injecting into areas with scars or stretch marks.
Choose a different site each time you give yourself an injection.

1 D

Clean your injection site.

Clean your injection site with an alcohol wipe. Let your skin dry before injecting.
Do not touch this area of skin again before injecting.

1 E

Remove prefilled syringe from tray.

To remove:

- Peel paper off of tray.
- Place the tray on your hand.
- Turn the tray over and gently press the middle of the tray's back to release the prefilled syringe into your palm.
- If the prefilled syringe does not release from the tray, gently press on the back of the tray.
  Do not pick up or pull the prefilled syringe by the plunger rod or gray needle cap. This could damage the syringe.
  Do not remove the gray needle cap from the prefilled syringe until you are ready to inject.
  Always hold the prefilled syringe by the syringe barrel.

1 F

Check the medicine and syringe.

Always hold the prefilled syringe by the syringe barrel.
Check that:

- the name REPATHA appears on the prefilled syringe label.
- the medicine in the prefilled syringe is clear and colorless to slightly yellow.
- the expiration date on the prefilled syringe has not passed. If the expiration date has passed, do not use the prefilled syringe.
  Do not use the prefilled syringe if any part of the prefilled syringe appears cracked or broken.
  Do not use the prefilled syringe if the gray needle cap is missing or not securely attached.
  Do not use the prefilled syringe if the medicine is cloudy or discolored or contains particles.

In any above cases, use a new prefilled syringe and call 1-844-REPATHA (1-844-737-2842) or visit www.REPATHA.com.

Step 2: Get ready
2 A | Carefully pull the gray needle cap straight out and away from your body. Do not leave the gray needle cap off for more than 5 minutes. This can dry out the medicine.
It is normal to see a drop of medicine at the end of the needle. |  | Place the gray needle cap in the sharps disposal container right away.
Do not twist or bend the gray needle cap. This can damage the needle.
Do not put the gray needle cap back onto the prefilled syringe.
Do not try to remove any air bubbles in the syringe before the injection.

2 B

Pinch your injection site to create a firm surface.

Pinch the skin firmly between your thumb and fingers, creating an area about 2 inches wide.

It is important to keep the skin pinched while injecting.

Step 3: Inject

3 A

Hold the pinch. Insert the needle into the skin using a 45 to 90 degree angle.

Do not place your finger on the plunger rod while inserting the needle.

3 B

Using slow and constant pressure, push the plunger rod all the way down until the prefilled syringe is empty. You may have to push harder on the plunger rod than for other injectable medicines.

3 C

When the prefilled syringe is empty, release your thumb, and gently lift the syringe out of the skin.

Do not put the gray needle cap back onto the used prefilled syringe.

Step 4: Finish

4 A

Place the used prefilled syringe in a sharps disposal container right away.

Do not reuse the used prefilled syringe.

Do not use any medicine that is left in the used prefilled syringe.

- Put the used prefilled syringe in an FDA-cleared sharps disposal container right away after use. Do not throw away (dispose of) the syringe in your household trash.
- If you do not have an FDA-cleared sharps disposal container, you may use a household container that is:
  - made of a heavy-duty plastic,
  - can be closed with a tight-fitting, puncture-resistant lid, without sharps being able to come out,
  - upright and stable during use,
  - leak-resistant, and
  - properly labeled to warn of hazardous waste inside the container.
- When your sharps disposal container is almost full, you will need to follow your community guidelines for the right way to dispose of your sharps disposal container. There may be state or local laws about how you should throw away used needles and syringes. For more information about safe sharps disposal, and for specific information about sharps disposal in the state that you live in, go to the FDA's website at: http://www.fda.gov/safesharpsdisposal.

Do not dispose of your used sharps disposal container in your household trash unless your community guidelines permit this. Do not recycle your used sharps disposal container.

Keep the used syringe and sharps container out of the sight and reach of children.

4 B

Check the injection site.

If there is blood, press a cotton ball or gauze pad on your injection site. Apply an adhesive bandage if needed.

Do not rub the injection site.

This Instructions for Use has been approved by the U.S. Food and Drug Administration.

Manufactured by:
Amgen Inc.
Thousand Oaks, CA 91320-1799
U.S. License Number 1080
© 2015-2016, 2021, 2024 Amgen Inc.
All rights reserved.
<part number> Revised: 11/2024 v4

Instructions for Use
Repatha® (ri-PAth-a)
(evolocumab)
prefilled single-dose syringe

Getting to know the prefilled syringe

Before use

After use

Needle is inside

Important

Before you use a prefilled single-dose syringe, read this important information:

- It is important that you do not try to give the injection until you have fully read and understood this Instructions for Use.
- Check the carton, prefilled syringe label, and prescription to make sure you have the correct medicine and dose.
- Check the expiration date on the REPATHA prefilled syringe carton: do not use if this date has passed.
- It is important that you do not try to give yourself or someone else the injection unless you have received training from your healthcare provider.
- The prefilled syringe is not made with natural rubber latex.

Storage of REPATHA:

- Keep the prefilled syringe in the original carton to protect from light during storage.
- Keep the prefilled syringe in the refrigerator between 36°F to 46°F (2°C to 8°C).
- If removed from the refrigerator, the prefilled syringe should be kept at room temperature at 68°F to 77°F (20°C to 25°C) in the original carton and must be used within 30 days. Place the prefilled syringe in a sharps disposal container if it has reached room temperature and has not been used within 30 days.
- Do not freeze the prefilled syringe or use a prefilled syringe that has been frozen.
- Do not store the prefilled syringe in extreme heat or cold. For example, avoid storing in your vehicle's glove box or trunk.

Do not:

- Do not use the prefilled syringe if the packaging is open or damaged.
- Do not remove the gray needle cap from the prefilled syringe until you are ready to inject.
- Do not use the prefilled syringe if it has been dropped onto a hard surface. Part of the prefilled syringe may be broken even if you cannot see the break. Use a new prefilled syringe and call 1-844-REPATHA (1-844-737-2842).
- Do not use the prefilled syringe after the expiration date.

A healthcare provider who knows how to use the prefilled syringe should be able to answer your questions. For more information, call 1-844-REPATHA (1-844-737-2842) or visit www.REPATHA.com.
Keep the prefilled syringe and all medicines out of the sight and reach of children.

Step 1: Prepare

1 A

Remove the prefilled syringe carton from the refrigerator and wait 30 minutes.

Wait at least 30 minutes for the prefilled syringe in the carton to reach room temperature before injecting.

Using the prefilled syringe at room temperature makes sure the full dose is delivered and allows for a more comfortable injection. Do not heat the syringe. Let it warm up on its own naturally.

Do not try to warm the prefilled syringe by using a heat source such as hot water or microwave.

Do not leave the prefilled syringe in direct sunlight.

Do not shake the prefilled syringe.

1 B

Gather all materials needed for your injection.

Wash your hands thoroughly with soap and water.

On a clean, well-lit, flat work surface, place:

- 1 REPATHA prefilled syringe in carton
- Alcohol wipes
- Cotton ball or gauze pad
- Adhesive bandage
- Sharps disposal container (see Step 4: Finish)

1 C

Choose your injection site.

You can use the:

- front of your thigh
- stomach (abdomen), except for a 2 inch area around your belly button

If someone else is giving you the injection, they can also use the outer area of the upper arm.
Do not choose an area where the skin is tender, bruised, red, or hard. Avoid injecting into areas with scars or stretch marks.
Choose a different site each time you give yourself an injection.

1 D

Clean your injection site.

Clean your injection site with an alcohol wipe. Let your skin dry before injecting.
Do not touch this area of skin again before injecting.

1 E

Remove prefilled syringe from tray.

To remove:

- Peel paper off of tray.
- Place the tray on your hand.
- Turn the tray over and gently press the middle of the tray's back to release the prefilled syringe into your palm.
- If the prefilled syringe does not release from the tray, gently press on the back of the tray.
  Do not pick up or pull the prefilled syringe by the plunger rod or gray needle cap. This could damage the syringe.
  Do not remove the gray needle cap from the prefilled syringe until you are ready to inject.
  Always hold the prefilled syringe by the syringe barrel.

1 F

Check the medicine and syringe.

Always hold the prefilled syringe by the syringe barrel.
Check that:

- the name REPATHA appears on the prefilled syringe label.
- the medicine in the prefilled syringe is clear and colorless to slightly yellow.
- the expiration date on the prefilled syringe has not passed. If the expiration date has passed, do not use the prefilled syringe.
  Do not use the prefilled syringe if any part of the prefilled syringe appears cracked or broken.
  Do not use the prefilled syringe if the gray needle cap is missing or not securely attached.
  Do not use the prefilled syringe if the medicine is cloudy or discolored or contains particles.

In any above cases, use a new prefilled syringe and call 1-844-REPATHA (1-844-737-2842) or visit www.REPATHA.com.

Step 2: Get ready
2 A | Carefully pull the gray needle cap straight out and away from your body. Do not leave the gray needle cap off for more than 5 minutes. This can dry out the medicine.
It is normal to see a drop of medicine at the end of the needle. |  | Place the gray needle cap in the sharps disposal container right away.
Do not twist or bend the gray needle cap. This can damage the needle.
Do not put the gray needle cap back onto the prefilled syringe.
Do not try to remove any air bubbles in the syringe before the injection.

2 B

Pinch your injection site to create a firm surface.

Pinch the skin firmly between your thumb and fingers, creating an area about 2 inches wide.

It is important to keep the skin pinched while injecting.

Step 3: Inject

3 A

Hold the pinch. Insert the needle into the skin using a 45 to 90 degree angle.

Do not place your finger on the plunger rod while inserting the needle.

3 B

Using slow and constant pressure, push the plunger rod all the way down until the prefilled syringe is empty. You may have to push harder on the plunger rod than for other injectable medicines.

3 C

When the prefilled syringe is empty, release your thumb, and gently lift the syringe out of the skin.

Do not put the gray needle cap back onto the used prefilled syringe.

Step 4: Finish

4 A

Place the used prefilled syringe in a sharps disposal container right away.

Do not reuse the used prefilled syringe.

Do not use any medicine that is left in the used prefilled syringe.

- Put the used prefilled syringe in an FDA-cleared sharps disposal container right away after use. Do not throw away (dispose of) the syringe in your household trash.
- If you do not have an FDA-cleared sharps disposal container, you may use a household container that is:
  - made of a heavy-duty plastic,
  - can be closed with a tight-fitting, puncture-resistant lid, without sharps being able to come out,
  - upright and stable during use,
  - leak-resistant, and
  - properly labeled to warn of hazardous waste inside the container.
- When your sharps disposal container is almost full, you will need to follow your community guidelines for the right way to dispose of your sharps disposal container. There may be state or local laws about how you should throw away used needles and syringes. For more information about safe sharps disposal, and for specific information about sharps disposal in the state that you live in, go to the FDA's website at: http://www.fda.gov/safesharpsdisposal.

Do not dispose of your used sharps disposal container in your household trash unless your community guidelines permit this. Do not recycle your used sharps disposal container.

Keep the used syringe and sharps container out of the sight and reach of children.

4 B

Check the injection site.

If there is blood, press a cotton ball or gauze pad on your injection site. Apply an adhesive bandage if needed.

Do not rub the injection site.

This Instructions for Use has been approved by the U.S. Food and Drug Administration.

Manufactured by:
Amgen Inc.
Thousand Oaks, CA 91320-1799
U.S. License Number 1080
© 2024 Amgen Inc.
All rights reserved.
<part number> Issued: 11/2024 v1

PRINCIPAL DISPLAY PANEL - 2 x 140 mg/mL Autoinjector Carton - NDC 72511-760-02

AMGEN

2 x Prefilled Single-Dose Autoinjectors

Repatha® SureClick®
(evolocumab)
Injection

repathainjection.com

140 mg/mL
Prefilled Autoinjector

For Subcutaneous Use Only

Sterile Solution – No Preservative
Store carton in refrigerator at 2°C to 8°C (36°F to 46°F).
Do Not Freeze or Shake.
Store in Carton to Protect from Light.
(see side panel for additional storage information)

140
mg/mL

CAUTION, See package insert
for full prescribing information
and Instructions for Use

This Product Contains
Dry Natural Rubber.

Do not re-use

Refrigerate
until ready
to use

Keep out of the sight
and reach of children.

Rx Only

U.S. License No. 1080
No U.S. standard of potency.

NDC 72511-760-02

PRINCIPAL DISPLAY PANEL - 1 x 140 mg/mL Autoinjector Carton - NDC 72511-760-91

AMGEN

1 x Prefilled Single-Dose Autoinjector

Repatha® SureClick®
(evolocumab)
Injection

Not for Sale

repathainjection.com

140 mg/mL
Prefilled Autoinjector

For Subcutaneous Use Only

Sterile Solution – No Preservative
Store carton in refrigerator at 2°C to 8°C (36°F to 46°F).
Do Not Freeze or Shake.
Store in Carton to Protect from Light.
(see side panel for additional storage information)

140
mg/mL

CAUTION, See package insert
for full prescribing information
and Instructions for Use

This Product Contains
Dry Natural Rubber.

Do not re-use

Refrigerate
until ready
to use

Keep out of the sight
and reach of children.

Rx Only

U.S. License No. 1080
No U.S. standard of potency.

NDC 72511-760-91

PRINCIPAL DISPLAY PANEL - 140 mg/mL Syringe Carton

1 x 1 mL Prefilled Syringe
NDC 72511-750-01

AMGEN®

Repatha®
(evolocumab)
Injection

140 mg/mL
Prefilled Syringe

For Subcutaneous Use Only

Store refigerated at 2°C to 8°C (36°F to 46°F). Do Not Freeze or Shake.
Store in Carton to Protect from Light.
(see side panel for additional storage information)

Sterile Solution – No Preservative

Do not re-use
Rx Only

CAUTION, See package insert for full prescribing
information and Instructions for Use

This Product Contains Dry Natural Rubber.

Keep out of the sight and reach of children

PRINCIPAL DISPLAY PANEL - Kit Carton

1 x 3.5 mL Prefilled Cartridge
1 On-Body Infusor
NDC 72511-770-01

AMGEN®

Repatha® Pushtronex® system
(evolocumab)
On-Body Infusor and Prefilled Cartridge

420 mg/3.5 mL

For Subcutaneous Use Only

Single-Dose Only

Sterile Solution – No Preservative
Store refrigerated at 2°C to 8°C (36°F to 46°F).
Do Not Freeze or Shake.
Store in Carton to Protect from Light.
(see side panel for additional storage information)

Keep out of the sight and reach of children.

Refer to Instructions for Use

Do Not Use if Package is Damaged

On-Body Infusor Sterilized
Using Ethylene Oxide

420 mg/
3.5 mL

MR Unsafe

Keep Dry

Do not re-use

Type BF Applied Part

Relative Humidity
Range is 15% to 85%

Rx Only

PRINCIPAL DISPLAY PANEL - 1 x 140 mg/mL Autoinjector Carton - NDC 72511-393-01

AMGEN

1 x Prefilled Single-Dose Autoinjector

Repatha® SureClick®
(evolocumab)
Injection

repathainjection.com

140 mg/mL
Prefilled Autoinjector

For Subcutaneous Use Only

Sterile Solution – No Preservative
Store carton in refrigerator at 2°C to 8°C (36°F to 46°F).
Do Not Freeze or Shake.
Store in Carton to Protect from Light.
(see side panel for additional storage information)

140
mg/mL

Not made with
natural rubber latex

CAUTION, See package insert
for full prescribing information
and Instructions for Use

Do not re-use

Refrigerate
until ready
to use

Keep out of the sight
and reach of children.

Rx Only

U.S. License No. 1080
No U.S. standard of potency.

NDC 72511-393-01

PRINCIPAL DISPLAY PANEL - 2 x 140 mg/mL Autoinjector Carton - NDC 72511-393-02

AMGEN

2 x Prefilled Single-Dose Autoinjectors

Repatha® SureClick®
(evolocumab)
Injection

repathainjection.com

140 mg/mL
Prefilled Autoinjector

For Subcutaneous Use Only

Sterile Solution – No Preservative
Store refrigerated at 2°C to 8°C (36°F to 46°F).
Do Not Freeze or Shake.
Store in Carton to Protect from Light.
(see side panel for additional storage information)

140
mg/mL

Not made with
natural rubber latex

CAUTION, See package insert
for full prescribing information
and Instructions for Use

Do not re-use

Refrigerate
until ready
to use

Keep out of the sight
and reach of children.

Rx Only

U.S. License No. 1080
No U.S. standard of potency.

NDC 72511-393-02

PRINCIPAL DISPLAY PANEL - 1 x 140 mg/mL Autoinjector Carton - NDC 72511-393-96

AMGEN

1 x Prefilled Single-Dose Autoinjector

Repatha® SureClick®
(evolocumab)
Injection

Not for Sale

repathainjection.com

140 mg/mL
Prefilled Autoinjector

For Subcutaneous Use Only

Sterile Solution – No Preservative
Store refrigerated at 2°C to 8°C (36°F to 46°F).
Do Not Freeze or Shake.
Store in Carton to Protect from Light.
(see side panel for additional storage information)

140
mg/mL

Not made with
natural rubber latex

CAUTION, See package insert
for full prescribing information
and Instructions for Use

Do not re-use

Refrigerate
until ready
to use

Keep out of the sight
and reach of children.

Rx Only

U.S. License No. 1080
No U.S. standard of potency.

NDC 72511-393-96

PRINCIPAL DISPLAY PANEL - 140 mg/mL Syringe Carton - NDC 72511-501-01

1 x 1 mL Prefilled Syringe
NDC 72511-501-01

AMGEN®

140
mg/mL

Repatha®
(evolocumab)
Injection

Not made
with natural
rubber latex

140 mg/mL
Prefilled Syringe

For Subcutaneous Use Only

Store refrigerated at 2°C to 8°C (36°F to 46°F). Do Not Freeze or Shake.
Store in Carton to Protect from Light.
(see side panel for additional storage information)

Sterile Solution – No Preservative

Rx Only

Do not re-use

CAUTION, See package insert for full prescribing
information and Instructions for Use

Keep out of the sight and reach of children

GTIN
SN
LOT
Exp.